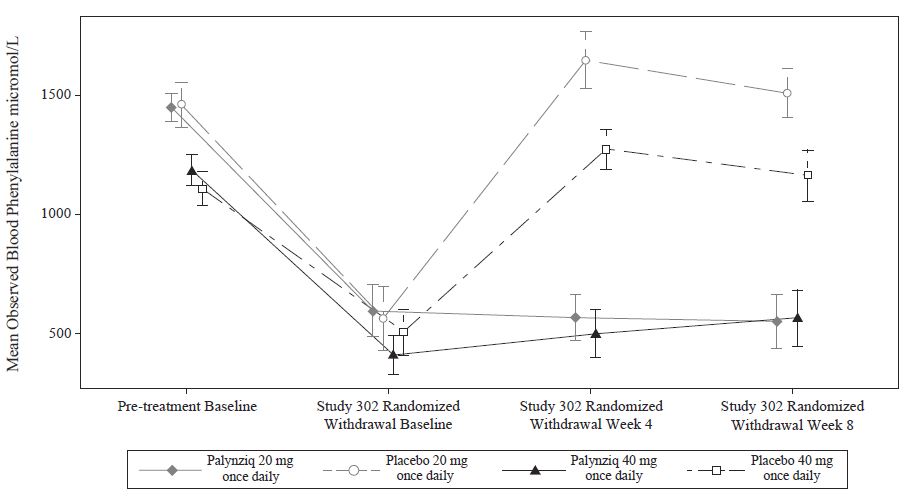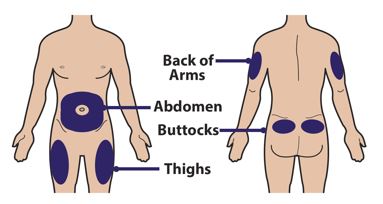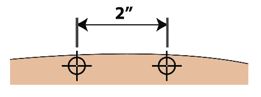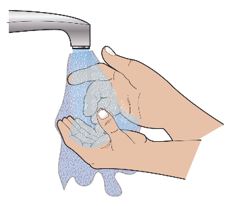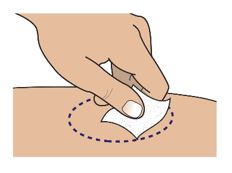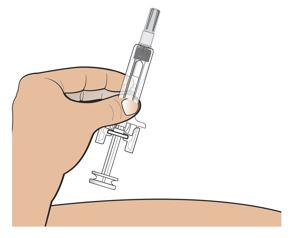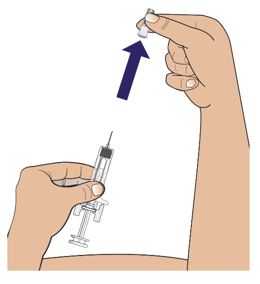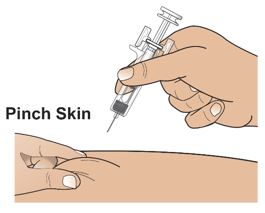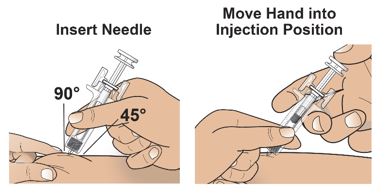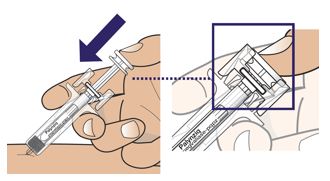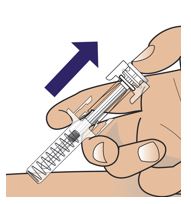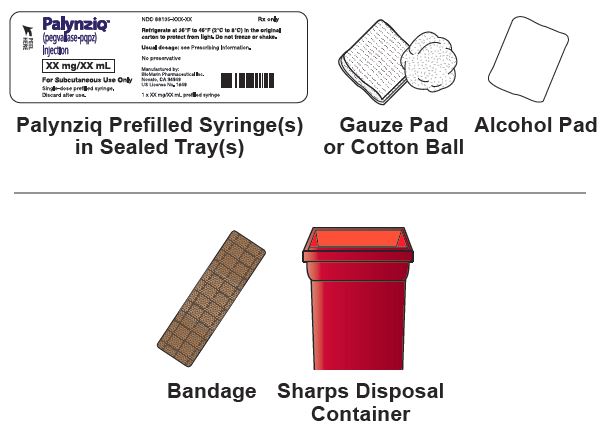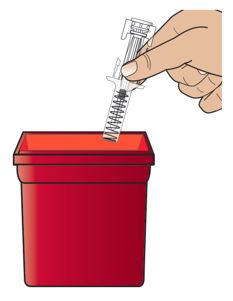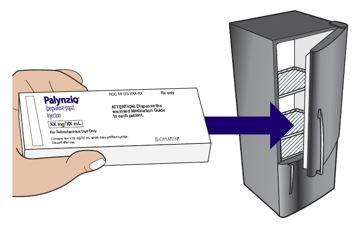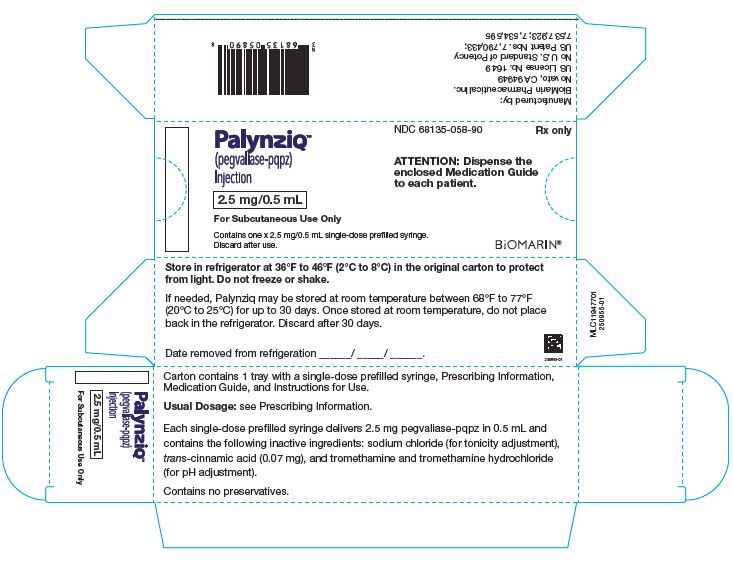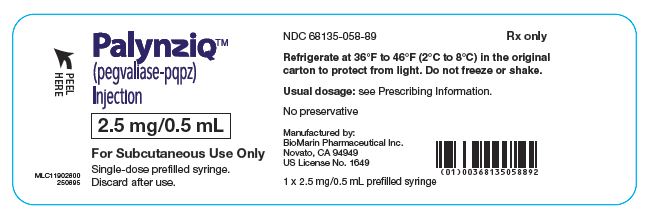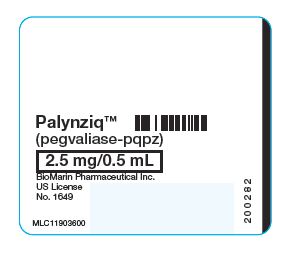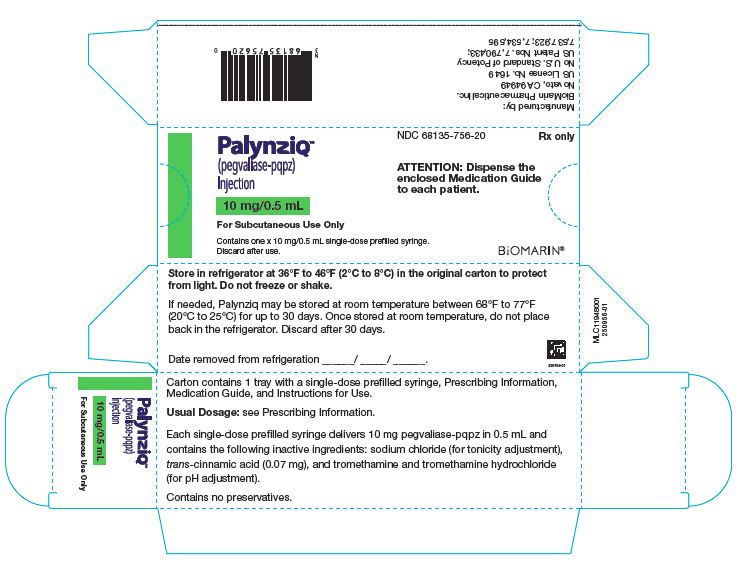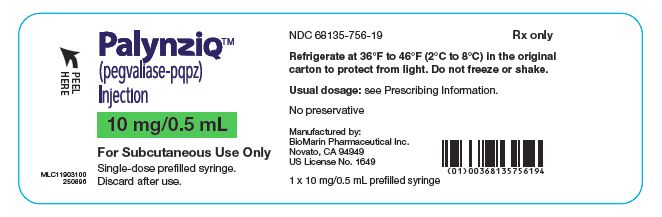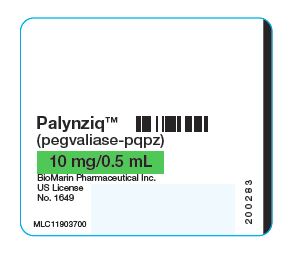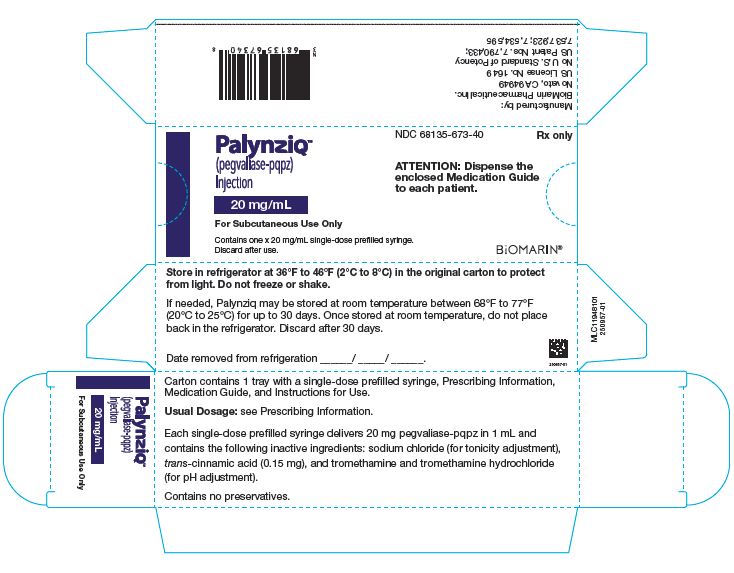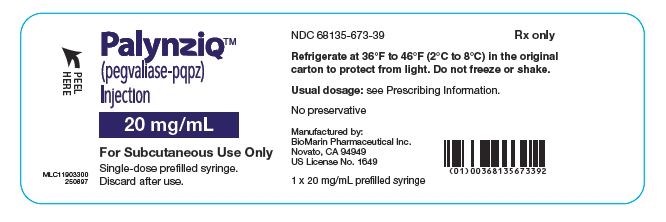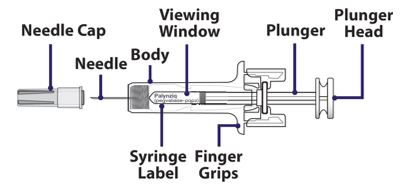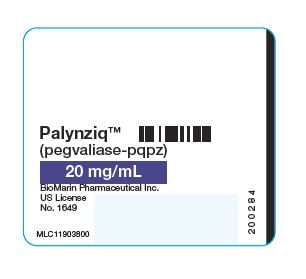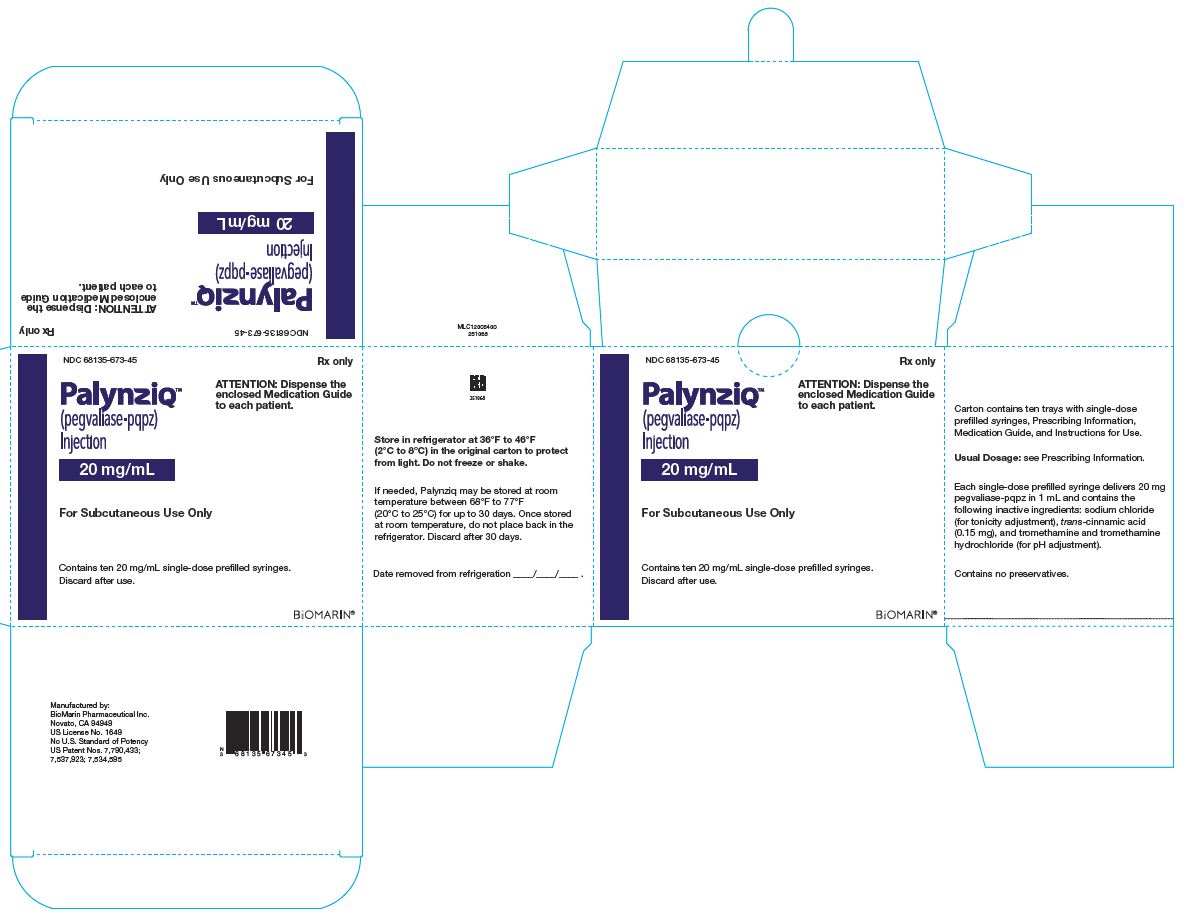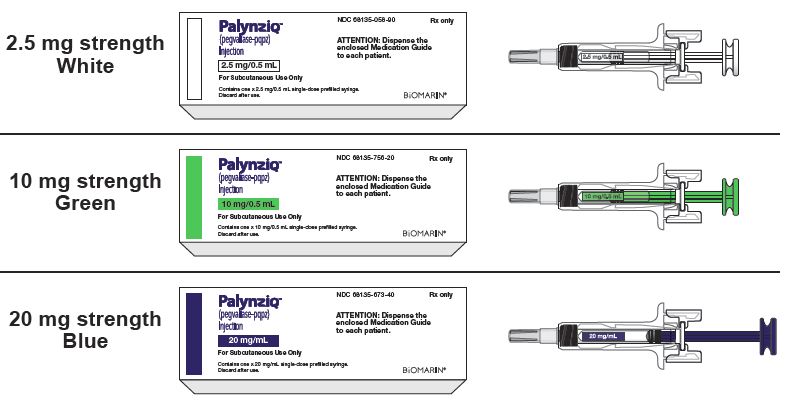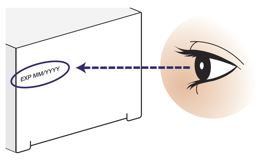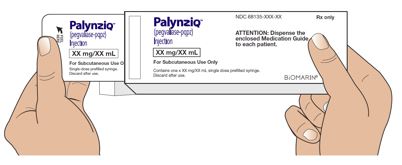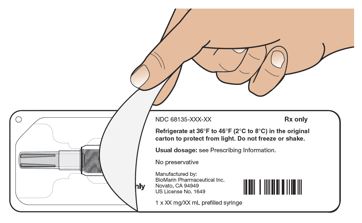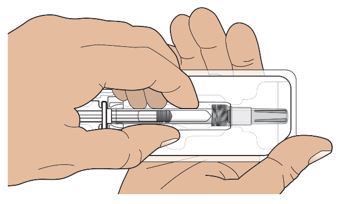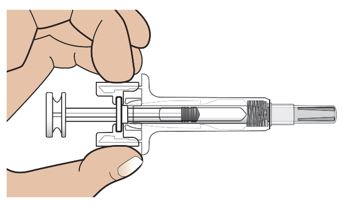 DRUG LABEL: Palynziq
NDC: 68135-058 | Form: INJECTION, SOLUTION
Manufacturer: BioMarin Pharmaceutical Inc.
Category: prescription | Type: HUMAN PRESCRIPTION DRUG LABEL
Date: 20251003

ACTIVE INGREDIENTS: PEGVALIASE 2.5 mg/0.5 mL

HIGHLIGHTS OF PRESCRIBING INFORMATION

These highlights do not include all the information needed to use PALYNZIQ safely and effectively. See full prescribing information for PALYNZIQ.
PALYNZIQ (pegvaliase-pqpz) injection, for subcutaneous use
Initial U.S. Approval: 2018

WARNING: RISK OF ANAPHYLAXIS

See full prescribing information for complete boxed warning.

- Anaphylaxis has been reported after administration of Palynziq and may occur at any time during treatment. (5.1)
- Administer the initial dose of Palynziq under the supervision of a healthcare provider equipped to manage anaphylaxis, and closely observe patients for at least 60 minutes following injection. Prior to self‑injection, confirm patient competency with self‑administration, and patient’s and observer’s (if applicable) ability to recognize signs and symptoms of anaphylaxis and to administer auto-injectable epinephrine, if needed. (2.4)
- Prescribe auto‑injectable epinephrine. Prior to first dose, instruct the patient and observer (if applicable) on its appropriate use. Instruct the patient to seek immediate medical care upon its use. Instruct patients to carry auto-injectable epinephrine with them at all times during Palynziq treatment. (2.4, 5.1)
- Palynziq is available only through a restricted program called the Palynziq REMS. (5.2)

RECENT MAJOR CHANGES

Warnings and Precautions (5.4) | 10/2025

1 INDICATIONS AND USAGE

Palynziq is a phenylalanine (Phe)‑metabolizing enzyme indicated to reduce blood Phe concentrations in adult patients with phenylketonuria who have uncontrolled blood Phe concentrations greater than 600 micromol/L on existing management. (1)

2 DOSAGE AND ADMINISTRATION

Dosage (2.1)

- Obtain baseline blood Phe concentration before initiating treatment.
- The recommended initial dosage is 2.5 mg subcutaneously once weekly for 4 weeks.
- Titrate the dosage in a step-wise manner over at least 5 weeks based on tolerability to achieve a dosage of 20 mg once daily. See full prescribing information for titration regimen.
- Assess patient tolerability, blood Phe concentration, and dietary protein and Phe intake throughout treatment.
- Consider increasing the dosage to 40 mg once daily in patients who have been on 20 mg once daily continuously for at least 24 weeks and who have not achieved blood Phe control (blood phenylalanine concentration less than or equal to 600 micromol/L).
- Consider increasing the dosage to a maximum of 60 mg once daily in patients who have been on 40 mg once daily continuously for at least 16 weeks and who have not achieved blood Phe control.
- Discontinue Palynziq in patients who have not achieved an adequate response after 16 weeks of continuous treatment with the maximum dosage of 60 mg once daily.
- Reduce the dosage and/or modify dietary protein and Phe intake, as needed, to maintain blood Phe concentrations within a clinically acceptable range and above 30 micromol/L.

Blood Phenylalanine Monitoring and Diet (2.2)

- Obtain blood Phe concentrations every 4 weeks until a maintenance dosage is established.
- Periodically monitor blood Phe concentrations during maintenance therapy.
- Counsel patients to monitor dietary protein and Phe intake, and adjust as directed by their healthcare provider.

Premedication (2.3, 5.1, 5.3)

- Consider premedication for hypersensitivity reactions.

Administration Instructions (2.4)

- Rotate injection sites. If more than one injection is needed for a single dose, the injection sites should be at least 2 inches away from each other.

3 DOSAGE FORMS AND STRENGTHS

Injection: 2.5 mg/0.5 mL, 10 mg/0.5 mL, and 20 mg/mL in a single-dose prefilled syringe. (3)

4 CONTRAINDICATIONS

None. (4)

5 WARNINGS AND PRECAUTIONS

Hypersensitivity Reactions, Other than Anaphylaxis: Management should be based on the severity of the reaction, recurrence, and clinical judgement, and may include dosage adjustment, temporary drug interruption, or treatment with antihistamines, antipyretics, and/or corticosteroids. (5.3)

Injection Site Infections: Serious injection site infections, including abscess, cellulitis, necrosis, and ulcer have been reported. Instruct patients to contact their healthcare provider if signs or symptoms of an infection develop, persist, or worsen. (5.4)

6 ADVERSE REACTIONS

Most common adverse reactions (at least 20% in either treatment phase) are: injection site reactions, arthralgia, hypersensitivity reactions, headache, generalized skin reactions lasting at least 14 days, nausea, abdominal pain, vomiting, cough, oropharyngeal pain, pruritus, diarrhea, nasal congestion, fatigue, dizziness, and anxiety. (6.1)

To report SUSPECTED ADVERSE REACTIONS, contact BioMarin Pharmaceutical Inc. at 1-866-906-6100, or FDA at 1-800-FDA-1088 or www.fda.gov/medwatch.

7 DRUG INTERACTIONS

Effect of Palynziq on Other PEGylated Products: Monitor for hypersensitivity reactions, including anaphylaxis, with concomitant treatment. (7.1)

8 USE IN SPECIFIC POPULATIONS

Pregnancy: May cause fetal harm. (8.1)

FULL PRESCRIBING INFORMATION

WARNING: RISK OF ANAPHYLAXIS

- Anaphylaxis has been reported after administration of Palynziq and may occur at any time during treatment [see Warnings and Precautions (5.1)].
- Administer the initial dose of Palynziq under the supervision of a healthcare provider equipped to manage anaphylaxis, and closely observe patients for at least 60 minutes following injection. Prior to self‑injection, confirm patient competency with self‑administration, and patient’s and observer’s (if applicable) ability to recognize signs and symptoms of anaphylaxis and administer auto‑injectable epinephrine, if needed [see Dosage and Administration (2.4)].
- Consider having an adult observer for patients who may need assistance in recognizing and managing anaphylaxis during Palynziq treatment. If an adult observer is needed, the observer should be present during and for at least 60 minutes after Palynziq administration, should be able to administer auto‑injectable epinephrine, and call for emergency medical support upon its use [see Warnings and Precautions (5.1)].
- Prescribe auto‑injectable epinephrine to all patients treated with Palynziq. Prior to the first dose, instruct the patient and observer (if applicable) how to recognize the signs and symptoms of anaphylaxis, how to properly administer auto‑injectable epinephrine, and to seek immediate medical care upon its use. Instruct patients to carry auto‑injectable epinephrine with them at all times during treatment with Palynziq [see Dosage and Administration (2.4), Warnings and Precautions (5.1)].
- Consider the risks and benefits of readministering Palynziq following an episode of anaphylaxis. If the decision is made to readminister Palynziq, readminister the first dose under the supervision of a healthcare provider equipped to manage anaphylaxis and closely observe the patient for at least 60 minutes following the dose [see Dosage and Administration (2.4), Warnings and Precautions (5.1)].
- Because of the risk of anaphylaxis, Palynziq is available only through a restricted program under a Risk Evaluation and Mitigation Strategy (REMS) called the Palynziq REMS [see Warnings and Precautions (5.2)].

1 INDICATIONS AND USAGE

Palynziq is indicated to reduce blood phenylalanine concentrations in adult patients with phenylketonuria (PKU) who have uncontrolled blood phenylalanine concentrations greater than 600 micromol/L on existing management.

2 DOSAGE AND ADMINISTRATION

2.1 Dosage

- Treatment with Palynziq should be managed by a healthcare provider experienced in the management of PKU.

- Obtain baseline blood phenylalanine concentration before initiating treatment.

Induction

The recommended initial induction dosage for Palynziq is 2.5 mg subcutaneously once weekly for 4 weeks. Administer the initial dose under the supervision of a healthcare provider [see Dosage and Administration (2.4)].

Titration

Titrate the Palynziq dosage in a step-wise manner, based on tolerability, over at least 5 weeks, to achieve a dosage of 20 mg subcutaneously once daily according to Table 1.

Maintenance

Therapeutic response may not be achieved until the patient is titrated to an effective maintenance dosage of Palynziq. Use the lowest effective and tolerated dosage of Palynziq.

Assess patient tolerability, blood phenylalanine concentrations, and dietary protein and phenylalanine intake throughout treatment.

Individualize the maintenance dosage to achieve blood phenylalanine control (blood phenylalanine concentrations less than or equal to 600 micromol/L), taking into account patient tolerability to Palynziq and dietary protein intake (see Table 1).

Maintain the Palynziq dosage at 20 mg once daily for at least 24 weeks. Consider increasing the Palynziq dosage to 40 mg once daily in patients who have been on 20 mg once daily continuously for at least 24 weeks without achieving blood phenylalanine control. Consider increasing the Palynziq dosage to a maximum of 60 mg once daily in patients who have been on 40 mg once daily continuously for at least 16 weeks without achieving blood phenylalanine control.

Discontinuation

Discontinue Palynziq in patients who have not achieved an adequate response after 16 weeks of continuous treatment with the maximum dosage of 60 mg once daily [see Clinical Studies (14)].

Table 1: Recommended Dosing Regimen
Treatment | Palynziq Dosage | Duration [Additional time may be required prior to each dosage escalation based on patient tolerability.]
Induction | 2.5 mg once weekly | 4 weeks
Titration | 2.5 mg twice weekly | 1 week
Titration | 10 mg once weekly | 1 week
Titration | 10 mg twice weekly | 1 week
Titration | 10 mg four times per week | 1 week
Titration | 10 mg once daily | 1 week
Maintenance [Individualize treatment to the lowest effective and tolerated dosage. Consider increasing to 40 mg once daily in patients who have not achieved a response with 20 mg once daily continuous treatment for at least 24 weeks. Consider increasing to a maximum of 60 mg once daily in patients who have not achieved a response with 40 mg once daily continuous treatment for at least 16 weeks [see Clinical Studies (14)].] | 20 mg once daily | 24 weeks
Maintenance [Individualize treatment to the lowest effective and tolerated dosage. Consider increasing to 40 mg once daily in patients who have not achieved a response with 20 mg once daily continuous treatment for at least 24 weeks. Consider increasing to a maximum of 60 mg once daily in patients who have not achieved a response with 40 mg once daily continuous treatment for at least 16 weeks [see Clinical Studies (14)].] | 40 mg once daily | 16 weeks
Maximum [Discontinue Palynziq in patients who have not achieved an adequate response after 16 weeks of continuous treatment at the maximum dosage of 60 mg once daily.] | 60 mg once daily | 16 weeks

Dose Reduction for Low Phenylalanine Concentrations

During titration and maintenance of Palynziq treatment, patients may experience blood phenylalanine concentrations below 30 micromol/L. For blood phenylalanine concentrations below 30 micromol/L, the dosage of Palynziq may be reduced and/or dietary protein and phenylalanine intake may be modified to maintain blood phenylalanine concentrations within a clinically acceptable range and above 30 micromol/L [see Dosage and Administration (2.2)].

Readministration Following Anaphylaxis

If the decision is made to readminister Palynziq after an anaphylaxis episode, administer the first dose following the anaphylaxis episode under the supervision of a healthcare provider equipped to manage anaphylaxis and closely observe the patient for at least 60 minutes following the dose. Subsequent dose titration should be based on patient tolerability and therapeutic response [see Warnings and Precautions (5.1)].

Missed Dose

If a dose is missed, instruct patients to take their next dose as scheduled and to not take two doses of Palynziq to make up for the missed dose.

2.2 Blood Phenylalanine Monitoring and Diet

After initiating treatment with Palynziq, obtain blood phenylalanine concentrations every 4 weeks until a maintenance dosage is established. After a maintenance dosage is established, periodic blood phenylalanine monitoring is recommended to assess blood phenylalanine control.

Monitor patients’ dietary protein and phenylalanine intake throughout treatment with Palynziq and counsel them on how to adjust their dietary intake, as needed, based on blood phenylalanine concentrations.

2.3 Premedication

For hypersensitivity reactions, consider premedication with an H1‑receptor antagonist, H2‑receptor antagonist, and/or antipyretic prior to Palynziq administration based upon individual patient tolerability [see Warnings and Precautions (5.1, 5.3)].

2.4 Administration Instructions

- Each prefilled syringe of Palynziq is intended for use as a single subcutaneous injection.
- Inspect Palynziq visually for particulate matter and discoloration prior to administration. Palynziq is a clear to slightly opalescent, colorless to pale yellow solution. Discard if discolored, cloudy, or if particulate matter is present.
- Prior to first dose of Palynziq, prescribe auto-injectable epinephrine, and instruct the patient and observer (if applicable) on how to recognize the signs and symptoms of anaphylaxis, how to properly administer auto-injectable epinephrine, and to seek immediate medical care upon its use.
- Perform initial administration(s) and/or readministration after an anaphylaxis episode under the supervision of a healthcare provider equipped to manage anaphylaxis, and closely observe patients for at least 60 minutes following injection [see Warnings and Precautions (5.1)]. Prior to self-injection, confirm patient competency with self‑administration.
- Consider having an adult observer for patients who may need assistance in recognizing and managing anaphylaxis during Palynziq treatment. If an adult observer is needed, the observer should be present during and for at least 60 minutes after each Palynziq administration, should be able to administer auto-injectable epinephrine, and to call for emergency medical support upon its use [see Warnings and Precautions (5.1)].
- The recommended injection sites for Palynziq are: the front middle of thighs and the abdomen at least 2 inches (five centimeters) away from the navel. If a caregiver is giving the injection, the top of buttocks and the back of the upper arms are also appropriate injection sites.
- Do not inject Palynziq into moles, scars, birthmarks, bruises, rashes, or areas where the skin is hard, tender, red, damaged, burned, inflamed, or tattooed. Check the injection site for redness, swelling, or tenderness.
- Rotate sites for subcutaneous injections of Palynziq. If more than one injection is needed for a single dose of Palynziq, the injection sites should be at least 2 inches away from each other. The second injection site can be on the same part of the body or a different part of the body.

3 DOSAGE FORMS AND STRENGTHS

Palynziq is a clear to slightly opalescent, colorless to pale yellow solution available as follows:

- Injection: 2.5 mg/0.5 mL single-dose prefilled syringe
- Injection: 10 mg/0.5 mL single-dose prefilled syringe
- Injection: 20 mg/mL single-dose prefilled syringe

4 CONTRAINDICATIONS

None.

5 WARNINGS AND PRECAUTIONS

5.1 Anaphylaxis

In clinical trials of Palynziq with induction/titration/maintenance dosing, 29 out of 285 (10%) patients experienced a total of 42 anaphylaxis episodes [see Adverse Reactions (6.1, 6.2)]. The exposure-adjusted rate of anaphylaxis was highest during the induction and titration phases (0.25 episodes/person‑years; 5% of patients with at least one episode) and decreased in the maintenance phase (0.05 episodes/person‑years; 7% of patients with at least one episode). Signs and symptoms of anaphylaxis reported in clinical trials of Palynziq included syncope, hypotension, hypoxia, dyspnea, wheezing, chest discomfort/chest tightness, tachycardia, angioedema (swelling of face, lips, eyes, tongue), throat tightness, skin flushing, rash, urticaria, pruritus, and gastrointestinal symptoms (vomiting, nausea, diarrhea). In clinical trials of Palynziq, anaphylaxis generally occurred within 1 hour after injection (81%; 34/42 episodes); however, delayed episodes also occurred up to 48 hours after Palynziq administration. Most episodes of anaphylaxis occurred within the first year of dosing (69%, 29/42 episodes), but cases also occurred after one year of dosing and up to 1604 days (4.4 years) into treatment. Management of anaphylaxis in Palynziq clinical trials included: administration of auto-injectable epinephrine (48%; 20/42 episodes), corticosteroids (55%; 23/42 episodes), antihistamines (57%; 24/42 episodes), and/or oxygen (5%; 2/42 episodes). Twenty one out of the 29 (72%) patients who experienced anaphylaxis were rechallenged with Palynziq and 6 out of the 21 patients who were rechallenged (29%) had recurrence of anaphylaxis. All anaphylaxis episodes resolved without sequelae.

Consider having an adult observer for patients who may need assistance in recognizing and managing anaphylaxis during Palynziq treatment. If an adult observer is needed, the observer should be present during and for at least 60 minutes after Palynziq administration, should be able to administer auto‑injectable epinephrine, and to call for emergency medical support upon its use.

Anaphylaxis requires immediate treatment with auto-injectable epinephrine. Prescribe auto‑injectable epinephrine to all patients receiving Palynziq and instruct patients to carry auto‑injectable epinephrine with them at all times during Palynziq treatment. Prior to the first dose, instruct the patient and observer (if applicable) on how to recognize the signs and symptoms of anaphylaxis, how to properly administer auto‑injectable epinephrine, and to seek immediate medical care upon its use. Consider the risks associated with auto-injectable epinephrine use when prescribing Palynziq. Refer to the auto‑injectable epinephrine prescribing information for complete information.

Consider the risks and benefits of readministering Palynziq following an episode of anaphylaxis. If the decision is made to readminister Palynziq, administer the first dose under the supervision of a healthcare provider equipped to manage anaphylaxis and closely observe the patient for at least 60 minutes following the dose. Subsequent Palynziq dose titration should be based on patient tolerability and therapeutic response [see Dosage and Administration (2.4)].

Consider premedication with an H1-receptor antagonist, H2-receptor antagonist, and/or antipyretic prior to Palynziq administration based upon individual patient tolerability [see Dosage and Administration (2.3)].

Palynziq is available only through a restricted program under a REMS [see Warnings and Precautions (5.2)].

5.2 Palynziq REMS Program

Palynziq is available only through a restricted program under a REMS called the Palynziq REMS, because of the risk of anaphylaxis [see Warnings and Precautions (5.1)].

Notable requirements of the Palynziq REMS include the following:

- Prescribers must be certified with the program by enrolling in the program and completing training.
- Prescribers must prescribe auto‑injectable epinephrine with Palynziq.
- Pharmacies must be certified with the program and must dispense only to patients who are authorized to receive Palynziq.
- Patients must enroll in the program and be educated about the risk of anaphylaxis by a certified prescriber to ensure they understand the risks and benefits of treatment with Palynziq.
- Patients must have auto‑injectable epinephrine available at all times while taking Palynziq.

Further information, including a list of qualified pharmacies, is available at www.PALYNZIQREMS.com or by telephone 1‑855‑758‑REMS (1‑855‑758‑7367).

5.3 Other Hypersensitivity Reactions

Hypersensitivity reactions, other than anaphylaxis [see Warnings and Precautions (5.1), Adverse Reactions (6.1, 6.2)], have been reported in 204 out of 285 (72%) patients treated with Palynziq. The exposure adjusted rate of other hypersensitivity reactions was highest during the induction and titration phases (4.3 episodes/person-year; 50% of patients with at least one adverse reaction) and decreased in the maintenance phase (1.3 episodes/person-year; 61% of patients with at least one adverse reaction).

Consider premedication with an H1‑receptor antagonist, H2‑receptor antagonist, and/or antipyretic prior to Palynziq administration based upon individual patient tolerability [see Dosage and Administration (2.3)]. Management of hypersensitivity reactions should be based on the severity of the reaction, recurrence of the reaction, and the clinical judgement of the healthcare provider, and may include dosage adjustment, temporary drug interruption, or treatment with antihistamines, antipyretics, and/or corticosteroids.

5.4 Injection Site Infections

Serious injection-site infections including abscess, cellulitis, necrosis, and ulcer have been reported with Palynziq in clinical trials and in the postmarketing setting. Some cases required hospitalization, surgical debridement, intravenous antibiotics, and discontinuation of Palynziq. Provide proper training to patients and/or caregivers on the use of aseptic injection technique. Advise patients to rotate injection sites with each dose and to check the site for redness, swelling, or tenderness. Instruct patients to contact their healthcare provider if signs or symptoms of an infection develop, persist, or worsen. Advise patients to not administer Palynziq into the affected area until the infection has resolved [see Dosage and Administration (2.4) and Adverse Reactions (6.1, 6.2)].

6 ADVERSE REACTIONS

The following serious adverse reactions are discussed below and in other sections of labeling:

- Anaphylaxis [see Warnings and Precautions (5.1)]
- Other Hypersensitivity Reactions [see Warnings and Precautions (5.3)]

6.1 Clinical Trial Experience

Because clinical trials are conducted under widely varying conditions, adverse reaction rates observed in the clinical trials of a drug cannot be directly compared to rates in the clinical trials of another drug and may not reflect the rates observed in practice.

The data described below reflect a total treatment exposure of 789 patient-years in 285 patients who received Palynziq in an induction/titration/maintenance regimen in clinical trials [see Clinical Studies (14)]. Of the 285 patients, 229 patients were exposed to Palynziq for 24 weeks, 209 patients were exposed for 1 year, 181 patients were exposed for 2 years, and 160 patients were exposed for 3 years or longer. The patient population was evenly distributed between male and female patients, the mean age was 29 years (range: 16 to 56 years), and 98% of patients were White.

The most common adverse reactions (at least 20% of patients in either treatment phase) were injection site reactions, arthralgia, hypersensitivity reactions, headache, generalized skin reactions lasting at least 14 days, nausea, abdominal pain, vomiting, cough, oropharyngeal pain, pruritus, diarrhea, nasal congestion, fatigue, dizziness, and anxiety.

Of the 285 patients exposed to Palynziq in an induction/titration/maintenance regimen in clinical trials, 44 (15%) patients discontinued treatment due to adverse reactions. The most common adverse reactions leading to treatment discontinuation were hypersensitivity reactions (6% of patients) including anaphylaxis (3% of patients), angioedema (1% of patients), arthralgia (4% of patients), generalized skin reactions lasting at least 14 days (2% of patients), and injection site reactions (1% of patients).

The most common adverse reactions leading to dosage reduction were arthralgia (15% of patients), hypersensitivity reactions (9% of patients), injection site reactions (4% of patients), alopecia (3% of patients), and generalized skin reactions lasting at least 14 days (2% of patients).

The most common adverse reactions leading to temporary drug interruption were hypersensitivity reactions (14% of patients), arthralgia (13% of patients), anaphylaxis (4% of patients), and injection site reactions (4% of patients).

Table 2 lists adverse reactions reported in at least 15% of patients treated with Palynziq in an induction/titration/maintenance dosage regimen in clinical trials, and illustrates the adverse reaction rates over time by treatment phase. Table 3 lists laboratory abnormalities reported in at least 10% of patients treated with Palynziq in an induction/titration/maintenance dosage regimen in clinical trials.

For these analyses, the induction/titration phase was defined as the time prior to reaching a stable dose (completing an 8‑week phase at the same dose level). Once a stable dosage was reached, patients were considered to be in the maintenance phase thereafter. Safety data for patients who reached the maintenance phase are included within either the induction/titration or maintenance phases depending on the onset date of the adverse reaction. Safety data for patients who did not reach the maintenance phase are included within the induction/titration phase. The maintenance phase includes data for patients who were previously on Palynziq and transitioned to placebo during the randomized withdrawal period of Study 302 [see Clinical Studies (14)].

Rates of adverse reactions (adjusted for duration of exposure) generally decreased over time and for some stayed relatively stable. In the maintenance phase, the rate of adverse reactions (adjusted for duration of exposure) in patients who reached the maintenance phase was comparable across dosages evaluated. The types and rate of adverse reactions reported during the maintenance phase in patients who received 20 mg once daily, 40 mg once daily, and 60 mg once daily were similar. During long-term treatment (greater than 36 months), the exposure-adjusted rates of adverse reactions decreased.

Rates of laboratory abnormalities (adjusted for duration of exposure) stayed relatively stable over time, except for complement C4 below lower limit of normal (LLN) and hs-CRP above 0.287 mg/dL over a 6 month period (both decreased over time) and hypophenylalaninemia (blood phenylalanine concentration below 30 micromol/L) on a single measurement (increased over time). There were no dose‑related trends in type or rate of laboratory abnormalities (adjusted for duration of exposure) reported during the maintenance phase in patients receiving 20 mg once daily, 40 mg once daily, or 60 mg once daily.

Table 2: Adverse Reactions [≥ 15% incidence in either treatment phase] Reported in at least 15% of PKU Patients Treated with Palynziq in an Induction/Titration/Maintenance Regimen in Clinical Trials – Incidence and Exposure-Adjusted Rates
Treatment Phase; Treatment Duration | Induction/Titration Phase; (N = 285); 141 person-years; Mean: 188 days; Median: 116 days; Range: 1 to 2266 days |  | Maintenance Phase; (N = 225); 652 person-years; Mean: 1087 days; Median: 1158 days; Range: 5 to 2017 days
Adverse Reaction | N (%) [N (%) = Number of patients with at least 1 Adverse Reaction (%); Rate = Exposure-Adjusted Rate of Adverse Reactions (Adverse Reactions/Person‑Years)] | Episodes; (Rate) | N (%) | Episodes; (Rate)
Injection site reactions [Includes injection site: reaction, erythema, pruritus, pain, bruising, rash, swelling, urticaria, induration, hemorrhage, edema, mass, inflammation, nodule, discoloration, warmth, hematoma, irritation, vesicles, hypersensitivity, papule, discomfort, scar, paresthesia, hypertrophy, extravasation, dryness, scab] | 252 (88%) | 2965 (21) | 166 (74%) | 2169 (3.3)
Arthralgia [Includes arthralgia, pain in extremity, back pain, musculoskeletal pain, neck pain] | 211 (74%) | 1049 (7.4) | 154 (68%) | 893 (1.4)
Hypersensitivity reactions [Includes rash, urticaria, anaphylaxis, rash generalized, hypersensitivity, rash erythematous, rash maculo-papular, rash pruritic, serum sickness, swelling face, dermatitis contact, swollen tongue, lip swelling, rash macular, pharyngeal edema, injection site hypersensitivity, eczema, drug eruption, dermatitis allergic, dermatitis, tongue edema, palatal edema, edema mouth, multiple allergies, lip edema, eye edema, exfoliative rash, drug hypersensitivity, dermatitis atopic, dermatitis acneiform, pruritus allergic, mouth swelling, implant site rash, gingival swelling, face edema, eyelid edema, eye swelling, dermatitis psoriasiform, dermatitis infected, conjunctivitis allergic, bronchospasm, angioedema, allergic sinusitis, allergic cough, eczema nummular, rhinitis allergic] | 153 (54%) | 634 (4.5) | 145 (64%) | 845 (1.3)
Headache [Includes headache, migraine, sinus headache] | 102 (36%) | 214 (1.5) | 126 (56%) | 1049 (1.6)
Generalized skin reaction lasting at least 14 days [Includes pruritus, rash, urticaria, dry skin, rash erythematous, erythema, cellulitis, rash macular, pruritus generalized, petechiae, dermatitis allergic, skin infection, skin induration, rash maculo-papular, rash generalized, pharyngeal edema, macule, granulomatous dermatitis, exfoliative rash, drug eruption, dermatitis atopic, dermatitis, xanthogranuloma, skin plaque, skin mass, skin lesion, skin hypopigmentation, skin hyperpigmentation, skin exfoliation, septal panniculitis,scar, rash pruritic, rash papular, psoriatic arthropathy, pruritus allergic, papule, necrobiosis lipoidica diabeticorum, furuncle, eczema, ecchymosis, dermatitis psoriasiform, dermatitis infected, blister, eczema nummular, granuloma, infected dermal cyst, lipohypertrophy, psoriasis, skin irritation] | 61 (21%) | 97 (0.7) | 93 (41%) | 186 (0.3)
Nausea | 52 (18%) | 68 (0.5) | 69 (31%) | 141 (0.2)
Abdominal pain [Includes abdominal pain, abdominal pain upper, abdominal discomfort] | 39 (14%) | 54 (0.4) | 67 (30%) | 162 (0.3)
Vomiting | 36 (13%) | 53 (0.4) | 68 (30%) | 139 (0.2)
Cough | 27 (9%) | 33 (0.2) | 67 (30%) | 100 (0.2)
Oropharyngeal pain | 38 (13%) | 45 (0.3) | 65 (29%) | 108 (0.2)
Pruritus | 58 (20%) | 102 (0.7) | 61 (27%) | 424 (0.7)
Diarrhea | 26 (9%) | 32 (0.2) | 61 (27%) | 116 (0.2)
Nasal congestion | 12 (4%) | 16 (0.1) | 61 (27%) | 87 (0.1)
Fatigue | 37 (13%) | 81 (0.6) | 55 (24%) | 110 (0.2)
Dizziness | 47 (16%) | 65 (0.5) | 48 (21%) | 100 (0.2)
Anxiety | 14 (5%) | 23 (0.2) | 48 (21%) | 100 (0.2)
Alopecia | 13 (5%) | 14 (0.1) | 43 (19%) | 62 (0.1)

Table 3: Laboratory Abnormalities Reported in at least 10% of PKU Patients Treated with Palynziq in an Induction/Titration/Maintenance Regimen in Clinical Trials – Incidence and Exposure-Adjusted Rates
Treatment Phase; Treatment Duration | Induction/Titration Phase; (N = 285); 141 person‑years; Mean: 188 days; Median: 116 days; Range: 1 to 2266 days |  | Maintenance Phase; (N = 225); 652 person‑years; Mean: 1087 days; Median: 1158 days; Range: 5 to 2017 days
Laboratory Measurement | N (%) [N (%) = Number of patients with at least 1 laboratory abnormality (%); Rate = Exposure-Adjusted Rate of Laboratory Abnormalities (Laboratory Abnormalities/Person‑Years)] | Episodes; (Rate) | N (%) | Episodes; (Rate)
Complement factor C3 below LLN | 195 (68%) | 453 (3.2) | 188 (84%) | 2259 (3.5)
C-reactive protein (CRP) above ULN | 182 (64%) | 359 (2.5) | 160 (71%) | 1414 (2.2)
Hypophenylalaninemia [Blood phenylalanine concentration below 30 micromol/L] on a single measurement | 53 (19%) | 216 (1.5) | 147 (65%) | 1553 (2.4)
Complement factor C4 below LLN | 177 (62%) | 318 (2.3) | 111 (49%) | 714 (1.1)
Hypophenylalaninemia on 2 or more consecutive measurements | 45 (16%) | 62 (0.4) | 111 (49%) | 204 (0.3)
Blood creatine phosphokinase (CPK) above ULN | 50 (18%) | 88 (0.6) | 108 (48%) | 377 (0.6)
Hs-CRP above 0.287 mg/dL over a 6 month period | 34 (12%) | 34 (0.4) | 36 (16%) | 46 (0.1)

LLN – lower limit of normal

ULN – upper limit of normal

Hs – high sensitivity

Description of Selected Adverse Reactions

Arthralgia

In clinical trials, 245 out of 285 (86%) patients experienced episodes consistent with arthralgia (includes back pain, musculoskeletal pain, pain in extremity, and neck pain).

Arthralgia episodes were more frequent during the induction/titration phase (7.4 episodes/patient-year) and decreased over time (1.4 episodes/patient-year in the maintenance phase).

Forty-four out of 285 (15%) patients had one episode of arthralgia, 32 (11%) patients had 2 episodes of arthralgia, 18 (6%) had 3 episodes of arthralgia, and 146 (51%) had 4 or more episodes of arthralgia. Arthralgia occurred as early as after the first dose of Palynziq and occurred at any time during treatment. The mean duration of arthralgia was 16 days (median: 3 days, range: 1 to 936 days), and 19% of arthralgia episodes had a duration of at least 14 days. Severe arthralgia (severe pain limiting self-care activities of daily living) was reported by 11 (4%) patients. In addition to arthralgia, other joint-related signs and symptoms reported were: joint swelling (24 patients; 8%), joint stiffness (22 patients; 8%), and musculoskeletal stiffness (20 patients; 7%). Arthralgia episodes were managed with medications (e.g., nonsteroidal anti-inflammatory drugs, glucocorticoids, and acetaminophen), Palynziq dosage reduction (4% of episodes), Palynziq interruption (4% of episodes), or Palynziq withdrawal (0.6% of episodes). 97% of arthralgia episodes were reported as resolved at the time of last observation (up to 77 months of follow‑up).

Injection Site Reactions

Injection site reactions were reported as early as after the first dose of Palynziq and occurred at any time during treatment. Injection site reactions were more frequent during the induction/titration phase (21 episodes/patient-years) and decreased over time (3 episodes/patient‑years in the maintenance phase). The mean duration of injection site reaction was 10 days (median: 2 days, range: 1 to 1612 days), and 8% of injection site reactions had a duration of at least 14 days. 99% of injection site reactions were reported as resolved at the time of last observation (up to 77 months of follow‑up).

Three injection site reactions consistent with granulomatous skin lesions were reported (each reaction occurring in one patient): granulomatous dermatitis (occurred after 464 days of Palynziq treatment and lasted 16 days), xanthogranuloma (occurred after 378 days of Palynziq treatment and lasted 638 days) was treated with a topical antihistamine, corticosteroid, and Palynziq treatment was discontinued, and necrobiosis lipoidica diabeticorum (occurred after 281 days of Palynziq treatment and lasted 281 days). Necrobiosis lipoidica diabeticorum was treated with steroid injections and complicated by Pseudomonas infection. All three injection site reactions resolved.

One patient reported soft tissue infection (occurred after 196 days of Palynziq treatment and lasted 8 days) associated with mesenteric panniculitis treated with antibiotics, which resulted in treatment discontinuation.

Generalized Skin Reactions (not limited to the injection site) Lasting at Least 14 Days

In clinical trials, 134 out of 285 (47%) patients treated with Palynziq experienced generalized skin reactions (not limited to the injection site) lasting at least 14 days. Mean duration of these reactions was 63 days (median: 37 days; range: 14 to 638 days). Generalized skin reactions were more frequent during the induction/titration phase (0.7 episodes/patient‑years), and decreased over time (0.3 episodes/patient-years in the maintenance phase).

The mean time from first dose of Palynziq to onset of skin reactions was 373 days (median: 213 days; range: 2 to 1970 days). 5% of these reactions persisted at least 180 days, and 86% of these reactions were reported as resolved at the time of last observation (up to 77 months of follow‑up).

Angioedema

In clinical trials, 22 out of 285 (8%) patients experienced 45 episodes of angioedema (symptoms included: pharyngeal edema, swollen tongue, lip swelling, mouth swelling, eyelid edema and face edema) occurring independent of anaphylaxis. Angioedema (included under Hypersensitivity in Table 2) was more frequent during the induction/titration phase (0.14 episodes/patient-year) and decreased over time (0.04 episodes/patient-year in the maintenance phase). Three patients discontinued treatment. All episodes resolved. Angioedema can present as a symptom of anaphylaxis [see Warnings and Precautions (5.1)].

Serum Sickness

In clinical trials, serum sickness was reported in 7 out of 285 (2%) patients. Serum sickness episodes were more frequent during the induction/titration phase (0.04 episodes/patient-year) and decreased over time (less than 0.01 episodes/patient-year during the maintenance phase). All serum sickness reactions resolved without sequelae (duration of serum sickness ranged from 1 to 8 days). Out of the 7 patients who experienced serum sickness, 5 patients continued treatment without a recurrence, and managed serum sickness with drug interruption, dosage reduction and/or concomitant medication. Two patients discontinued treatment.

6.2 Post-Marketing Experience

The following adverse reactions have been identified during post-approval use of Palynziq. Because these reactions are reported voluntarily from a population of uncertain size, it is not always possible to reliably estimate their frequency or establish a causal relationship to drug exposure.

Administration site conditions: injection site infection, cellulitis, necrosis, and abscess.

6.3 Immunogenicity

As with all therapeutic proteins, there is potential for immunogenicity. The detection of antibody formation is highly dependent on the sensitivity and specificity of the assay. Additionally, the observed incidence of antibody (including neutralizing antibody) positivity in an assay may be influenced by several factors, including assay methodology, sample handling, timing of sample collection, concomitant medications, and underlying disease. For these reasons, comparison of the incidence of antibodies to Palynziq in the studies described below with the incidence of antibodies in other studies or to other products may be misleading.

All patients treated with Palynziq developed a sustained total anti-drug antibody (TAb) response with a majority of patients (91%; N = 235/258) developing that response by Week 4 of treatment. Mean TAb titers peaked 2 weeks after Palynziq initiation and remained elevated throughout treatment (greater than 3 years after treatment initiation). Anti-phenylalanine ammonia lyase (PAL) IgM antibodies were detected in a majority of patients (98%; N = 265/270) by 2 months after treatment initiation, with incidence declining over time to 67% at 36 months (N = 114/171). Anti‑PAL IgG antibodies were detected in almost all patients (N = 226/227) by 4 months after treatment initiation. Mean anti-PAL IgM and IgG titers peaked at approximately 3 and 6 months, respectively, after treatment initiation and remained elevated throughout treatment (greater than 3 years after treatment initiation). Drug-induced anti-PEG IgM and IgG antibodies were detected in the majority of patients (98%; N = 277/284 for IgM; and 278/284 for IgG) with mean titers for both peaking at 1 to 3 months after treatment initiation [see Drug Interactions (7.1)]. Neutralizing antibodies (NAb) capable of inhibiting PAL enzyme activity were detected on at least one measurement in the majority of patients (89%; N = 253/284) over time. Mean NAb titers peaked and reached a plateau at 16 to 20 weeks of treatment and then remained present throughout treatment (greater than 3 years after treatment initiation).

Twenty-seven of 29 patients who had anaphylaxis were tested for anti‑pegvaliase‑pqpz IgE antibodies, which recognize the PEGylated protein product. Of the 27 patients tested for anti‑pegvaliase‑pqpz IgE antibodies, 26 patients tested negative. The one patient who tested positive for anti‑pegvaliase‑pqpz IgE antibodies on the screening test did not have sufficient sample to confirm IgE positivity. This patient tested negative for anti‑pegvaliase‑pqpz IgE at routine visits prior to and after the anaphylaxis episode (not at times of anaphylaxis). Sixty‑seven of 285 patients in clinical trials were tested for both anti‑PAL IgE antibodies, which recognize the recombinant PAL protein, and for anti‑pegvaliase‑pqpz IgE antibodies during routine study visits (not at times of anaphylaxis episodes) or during additional visits for hypersensitivity reactions. Of those 67 patients, 5 (8%) tested positive at least once for anti‑PAL IgE antibodies but negative for anti‑pegvaliase‑pqpz IgE antibodies.

The highest frequency of hypersensitivity reactions (consistent with a Type III immune complex-mediated hypersensitivity mechanism) occurred within the first 6 months of Palynziq treatment when the mean circulating immune complex (CIC) concentrations were at their highest and mean complement C3 and C4 concentrations were at their lowest. Mean CIC concentrations decreased and complement levels increased over time as the exposure-adjusted rate of hypersensitivity reactions decreased. IgG and IgM CIC concentrations were above the upper limit of normal in 63% (N = 164/259) and 42% of patients (N = 109/259), respectively, at 12 weeks of Palynziq treatment and returned towards baseline with long-term treatment (greater than 3 years after treatment initiation). 61% of patients (N = 110/180) had complement C3 concentrations less than lower limit of normal (LLN) at 6 months after treatment initiation and 38% of patients (N = 94/248) had complement C4 concentrations less than LLN at 3 months after treatment initiation. The incidence of low complement C3 and C4 concentrations decreased over time, but approximately 35% (N = 34/96) and 12% (N = 11/96) of patients had low C3 and C4 concentrations, respectively, at 36 months after treatment initiation.

Higher antibody responses for all antibody analytes, including NAb, were associated with lower mean trough pegvaliase‑pqpz concentrations and with higher blood phenylalanine concentrations. Hypersensitivity reactions occurred more frequently in patients with higher antibody titers for some but not all antibody analytes. Patients with higher mean change in IgG CIC concentrations from pre-treatment baseline tended to have higher discontinuation rates than patients with lower mean change in IgG CIC concentrations. Mean antibody titers for anti‑PAL IgG and IgM, TAb, and NAb remained relatively stable with long-term treatment.

7 DRUG INTERACTIONS

7.1 Effect of Palynziq on Other PEGylated Products

In a single dose study of Palynziq in adult patients with PKU, two patients receiving concomitant injections of medroxyprogesterone acetate suspension (a formulation containing PEG 3350) experienced a hypersensitivity reaction. One of the two patients experienced a hypersensitivity reaction on day 15 after a single Palynziq dosage of 0.67 mg within 15 minutes following medroxyprogesterone acetate injectable suspension, and subsequently experienced anaphylaxis on day 89 within 30 minutes after the next dose of medroxyprogesterone acetate injectable suspension. The other patient experienced a hypersensitivity reaction on day 40 after a single Palynziq dosage of 0.08 mg within 10 minutes following medroxyprogesterone acetate injectable suspension. Both patients had high anti‑PEG IgG antibody titers at or around the time of the hypersensitivity reactions.

In Palynziq clinical trials, the majority of patients developed anti‑PEG IgM and IgG antibodies after treatment with Palynziq [see Adverse Reactions (6.2)]. The clinical effects of concomitant treatment with different PEGylated products is unknown. Monitor patients treated with Palynziq and concomitantly with other PEGylated products for hypersensitivity reactions including anaphylaxis.

8 USE IN SPECIFIC POPULATIONS

8.1 Pregnancy

Risk Summary

Based on findings in studies of pregnant animals without PKU treated with pegvaliase-pqpz, Palynziq may cause fetal harm when administered to a pregnant woman. Limited available data with pegvaliase-pqpz use in pregnant women are insufficient to inform a drug-associated risk of adverse developmental outcomes. There are risks to the fetus associated with poorly controlled phenylalanine concentrations in women with PKU during pregnancy including increased risk for miscarriage, major birth defects (including microcephaly, major cardiac malformations), intrauterine fetal growth retardation, and future intellectual disability with low IQ; therefore, phenylalanine concentrations should be closely monitored in women with PKU during pregnancy (see Clinical Considerations and Data). Advise pregnant women of the potential risks to the fetus.

A reproduction study in pregnant rabbits treated with pegvaliase‑pqpz demonstrated a high incidence of fetal malformations throughout the skeletal system, and in kidneys, lungs, and eyes. Embryo‑fetal toxicity (increased resorptions and reduced fetal weight) was also observed. These effects occurred at 5 times the maximum recommended daily dose and were associated with strong signs of maternal toxicity, including marked reductions in weight gain and food consumption, and death. A reproduction study in pregnant rats treated with pegvaliase‑pqpz demonstrated an increase in skeletal variations, with no malformations observed. The effects in rats occurred at 2.8 times the maximum recommended daily dose. In a pre-/post-natal development study in rats, pegvaliase‑pqpz produced reduced survival of offspring during lactation, decreases in pup weight and litter size, and delayed sexual maturation of offspring when administered daily at 13 times the maximum recommended daily dose. The effects on rat embryo‑fetal and post-natal development were also associated with maternal toxicity.

All pregnancies have a background risk of major birth defects, pregnancy loss, or other adverse pregnancy outcomes. In the U.S. general population, the estimated background risk of major birth defects and miscarriage in clinically recognized pregnancies is 2 to 4% and 15 to 20%, respectively. The estimated background risk of major birth defects and miscarriage in pregnant women with PKU who maintain blood phenylalanine concentrations greater than 600 micromol/L during pregnancy is greater than the corresponding background risk for pregnant women without PKU.

There is a pregnancy surveillance program for Palynziq. If Palynziq is administered during pregnancy, or if a patient becomes pregnant while receiving Palynziq or within one month following the last dose of Palynziq, healthcare providers should report Palynziq exposure by calling 1-866-906-6100.

Clinical Considerations

Disease-Associated Maternal and/or Embryo-Fetal Risk

Uncontrolled blood phenylalanine concentrations before and during pregnancy are associated with an increased risk of adverse pregnancy outcomes and fetal adverse effects. To reduce the risk of hyperphenylalaninemia-induced fetal adverse effects, blood phenylalanine concentrations should be maintained between 120 and 360 micromol/L during pregnancy and during the 3 months before conception [see Dosage and Administration (2.2)].

Dose Adjustments During Pregnancy and the Postpartum Period

Phenylalanine concentrations below 30 micromol/L in pregnant women with PKU treated with Palynziq may be associated with adverse fetal outcomes. Monitor blood phenylalanine concentrations during pregnancy and adjust the dosage of Palynziq or modify dietary protein and phenylalanine intake to avoid blood phenylalanine concentrations below 30 micromol/L [see Dosage and Administration (2.2)].

Data

Human Data

Uncontrolled Maternal PKU: Available data from the Maternal Phenylketonuria Collaborative Study on 468 pregnancies and 331 live births in pregnant women with PKU demonstrated that uncontrolled phenylalanine concentrations above 600 micromol/L are associated with an increased risk for miscarriage, major birth defects (including microcephaly, major cardiac malformations), intrauterine fetal growth retardation, and future intellectual disability with low IQ.

Limited data from case reports of Palynziq use in pregnant women are insufficient to determine a drug‑associated risk of adverse developmental outcomes.

Animal Data

All developmental toxicity studies were conducted in animals (rats and rabbits) without PKU, in which treatment with pegvaliase-pqpz produced a dose-dependent reduction in maternal blood phenylalanine concentrations. At doses that produced maternal toxicity and/or effects on embryo-fetal development, the maternal plasma phenylalanine concentrations were markedly reduced compared to the control group. The contribution of maternal phenylalanine depletion to the incidence of embryo‑fetal developmental effects was not evaluated.

Subcutaneous administration of 5 mg/kg/day pegvaliase‑pqpz (5 times the maximum recommended daily dose based on bodyweight [mg/kg]) in pregnant rabbits during the period of organogenesis produced embryo‑lethality (increased resorptions), marked reduction in fetal weight, and fetal malformations. The malformations included multiple external abnormalities of the head, body and limbs, multiple soft tissue malformations (reduced size or absence of kidneys, diaphragmatic hernia, corneal opacity, discoloration or reduced size of eyes, and reduced size of lungs) and multiple skeletal malformations of the craniofacial bones, vertebrae, sternebrae, ribs, pelvis, limbs, and digits. An increase in variations and delayed ossification was also observed in all skeletal regions. The adverse developmental effects were associated with maternal toxicity, as indicated by marked impairment of weight gain and food consumption. Deaths associated with weight loss and abortion occurred in 8% of the pregnant rabbits treated with 5 mg/kg/day pegvaliase‑pqpz.

Subcutaneous administration of 2 mg/kg/day pegvaliase‑pqpz (2 times the maximum recommended daily dose based on bodyweight [mg/kg]) in pregnant rabbits had no adverse effects on embryo-fetal development. Systemic exposure to pegvaliase‑pqpz was detected in fetuses from rabbits treated with 2 or 5 mg/kg/day.

Pegvaliase‑pqpz increased fetal alterations when administered daily in pregnant rats at doses of 8 mg/kg subcutaneously and higher (2.8 times the human steady-state area under the curve [AUC] at the maximum recommended daily dose) during a 28‑day premating period, mating, and through the period of organogenesis. The fetal alterations were limited to skeletal variations such as cervical ribs, bifid centra of lumbar and thoracic vertebrae, and incomplete ossification of squamosal bones, frontal bones, lumbar vertebra arch, and ribs. Daily administration of 20 mg/kg subcutaneously (13 times the human steady-state AUC at the recommended maximum daily dose) to pregnant rats produced reductions in litter sizes and fetal weights, which was associated with maternal toxicity (decreased body weight, ovarian weight, and food consumption). The decrease in litter sizes at 20 mg/kg subcutaneously was secondary to reductions in corpora lutea and implantations. Systemic exposure to pegvaliase‑pqpz was detected in fetuses from rats treated with 20 mg/kg of pegvaliase‑pqpz (13 times the human steady-state AUC at the recommended maximum daily dose). Subcutaneous administration of 2 mg/kg/day pegvaliase‑pqpz (less than the human steady state AUC at the maximum recommended daily dose) in pregnant rats had no adverse effects on embryo‑fetal development.

Pegvaliase-pqpz decreased pup weight, litter size, and survival of offspring during lactation, and delayed sexual maturation of offspring when administered daily in rats at 20 mg/kg subcutaneously (13 times the human steady-state AUC at the recommended maximum daily dose), with dosing starting before mating and continuing through lactation. The effects in offspring were associated with maternal toxicity. No effects in offspring were observed at 8 mg/kg/day subcutaneously (2.8 times the human steady-state AUC at the recommended maximum daily dose). A follow-up study of the same design evaluated additional parameters of physical and neurobehavioral development in offsprings; No effects of pegvaliase‑pqpz were noted at the maternal NOAEL dose of 8 mg/kg/day.

8.2 Lactation

Risk Summary

There are no data on the presence of pegvaliase-pqpz in human milk, the effects on the breastfed infant, or the effects on milk production. A pre-/post-natal study in rats showed that pegvaliase-pqpz is present in rat milk and that administration of pegvaliase-pqpz during lactation decreased pup weight and survival [see Use in Specific Populations (8.1)]. However, systemic absorption of pegvaliase-pqpz was not detected in the rat pups. Palynziq may cause low phenylalanine concentrations in human milk. The developmental and health benefits of breastfeeding should be considered along with the clinical need for Palynziq treatment and any potential adverse effect on the breastfed infant from Palynziq or from the underlying condition (see Clinical Considerations).

Clinical Considerations

Monitor blood phenylalanine concentrations in breastfeeding women treated with Palynziq.

8.4 Pediatric Use

The safety and effectiveness of Palynziq in pediatric patients have not been established.

8.5 Geriatric Use

Clinical studies of Palynziq did not include patients aged 65 years and older.

11 DESCRIPTION

Pegvaliase-pqpz is a phenylalanine-metabolizing enzyme that is composed of recombinant phenylalanine ammonia lyase (rAvPAL) conjugated to N-hydroxysuccinimide (NHS)-methoxypolyethylene glycol (PEG). rAvPAL is manufactured in Escherichia coli bacteria transformed with a plasmid containing the phenylalanine ammonia lyase (PAL) gene derived from Anabaena variabilis. During the rAvPAL manufacturing process, fermentation is carried out in nutrient medium containing the antibiotic kanamycin. However, kanamycin is cleared in the manufacturing process and is not detectable in the final product. rAvPAL is a homotetrameric protein with a molecular weight of 62 kD per monomer. To produce pegvaliase-pqpz, an average of nine (9) 20 kD PEG molecules are covalently bound (or conjugated) to each monomer of rAvPAL. The total molecular weight of pegvaliase‑pqpz (rAvPAL‑PEG) is approximately 1000 kD.

Palynziq (pegvaliase‑pqpz) injection, intended for subcutaneous injection, is a clear to slightly opalescent, colorless to pale yellow, sterile, preservative-free solution and is formulated at pH 6.6 to 7.4.

Palynziq is provided in a single-dose prefilled syringe and is available in three dosage strengths: 2.5 mg/0.5 mL, 10 mg/0.5 mL, and 20 mg/mL. Palynziq contents for each dosage strength are summarized in Table 4.

Table 4: Contents of Palynziq
Strength | Total Contents per Prefilled Syringe
Palynziq 2.5 mg/0.5 mL; prefilled syringe | 2.5 mg pegvaliase-pqpz (expressed as the amount of rAvPAL conjugated to 7.25 mg of 20 kD PEG in 0.5 mL Water for Injection, USP) and contains the following inactive ingredients: sodium chloride (for tonicity adjustment), trans-cinnamic acid (0.07 mg), and tromethamine and tromethamine hydrochloride (for pH adjustment).
Palynziq 10 mg/0.5 mL; prefilled syringe | 10 mg pegvaliase-pqpz (expressed as the amount of rAvPAL conjugated to 29 mg of 20 kD PEG in 0.5 mL Water for Injection, USP) and contains the following inactive ingredients: sodium chloride (for tonicity adjustment), trans-cinnamic acid (0.07 mg), and tromethamine and tromethamine hydrochloride (for pH adjustment).
Palynziq 20 mg/mL; prefilled syringe | 20 mg pegvaliase-pqpz (expressed as the amount of rAvPAL conjugated to 58 mg of 20 kD PEG in 1 mL Water for Injection, USP) and contains the following inactive ingredients: sodium chloride (for tonicity adjustment), trans-cinnamic acid (0.15 mg), and tromethamine and tromethamine hydrochloride (for pH adjustment).

12 CLINICAL PHARMACOLOGY

12.1 Mechanism of Action

Pegvaliase-pqpz is a PEGylated phenylalanine ammonia lyase (PAL) enzyme that converts phenylalanine to ammonia and trans‑cinnamic acid. It substitutes for the deficient phenylalanine hydroxylase (PAH) enzyme activity in patients with PKU and reduces blood phenylalanine concentrations.

12.2 Pharmacodynamics

Palynziq treatment of adult patients with PKU resulted in the reduction of blood phenylalanine concentrations from pre-treatment baseline [see Clinical Studies (14)]. The reduction of blood phenylalanine concentrations diminished with decreased pegvaliase‑pqpz plasma concentrations.

12.3 Pharmacokinetics

The pharmacokinetics of pegvaliase‑pqpz exhibit high inter-patient and intra-patient variability due to the heterogeneity of the immune response in adult patients with PKU. Higher antibody titers correlated with higher apparent clearance of pegvaliase‑pqpz. In the first eight weeks of induction/titration treatment, plasma pegvaliase‑pqpz concentrations were low to not measurable. At steady state during maintenance treatment with Palynziq 20 mg, 40 mg, and 60 mg subcutaneously once daily, the mean ± SD (range) plasma trough pegvaliase‑pqpz concentrations were: 11.2 ± 9.0 (0.21 to 29.6) mg/L, 10.4 ± 12.7 (0.18 to 43.1) mg/L and 4.8 ± 10.7 (0 to 39.7) mg/L, respectively. The following pharmacokinetic parameters were observed in adult patients with PKU treated with Palynziq at maintenance dosages of 20 mg once daily and 40 mg once daily.

Absorption

The median Tmax was approximately 8 hours. The mean ± SD (range) peak concentration (Cmax) at steady state was: 14.0 ± 16.3 (0.26 to 68.5) mg/L and 16.7 ± 19.5 (0.24 to 63.8) mg/L, respectively.

Distribution

The mean ± SD (range) apparent volume of distribution was 26.4 ± 64.8 (1.8 to 241) L and 22.2 ± 19.7 (3.1 to 49.5) L, respectively.

Elimination

The mean ± SD (range) apparent clearance at steady state was 0.39 ± 0.87 (0.018 to 3.66) L/h and 1.25 ± 2.46 (0.034 to 8.88) L/h, respectively. The mean ± SD (range) half-life was 47 ± 42 (14 to 132) hours and 60 ± 45 (14 to 127) hours, respectively.

Metabolism

The metabolism of phenylalanine ammonia lyase is expected to occur via catabolic pathways and be degraded into small peptides and amino acids.

Excretion

The route of elimination of pegvaliase‑pqpz has not been studied in humans.

13 NONCLINICAL TOXICOLOGY

13.1 Carcinogenesis, Mutagenesis, Impairment of Fertility

Carcinogenicity and genotoxicity studies have not been performed with pegvaliase‑pqpz. Based on its mechanism of action, pegvaliase‑pqpz is not expected to be tumorigenic.

Pegvaliase-pqpz produced impaired fertility in female rats at 20 mg/kg/day subcutaneously (13 times the human steady-state AUC at the maximum recommended daily dose), as indicated by decreases in corpora lutea, implantations, and litter size. These effects were associated with maternal toxicity (decreased body weight, ovarian weight, and food consumption). No effects on mating or fertility were observed in female rats with 8 mg/kg/day subcutaneously (2.8 times the human steady-state AUC at the maximum recommended daily dose) or in male rats with 20 mg/kg/day subcutaneously.

13.2 Animal Toxicology and/or Pharmacology

In rats without PKU treated with pegvaliase-pqpz, dose-dependent vacuolation in multiple organs and tissues was observed in the 4‑ and 26‑week repeat dose toxicity studies at doses of 8 mg/kg subcutaneously or greater administered twice weekly (less than the human steady state AUC at the maximum recommended daily dose). Vacuolation occurred in renal tubule cells and in histiocytic cells of the liver, spleen, testes, adrenal cortex, mesenteric lymph node, and mandibular lymph node. Vacuolation in histiocytes of the affected organs and tissues persisted after cessation of treatment. The vacuolation observed in these studies was not associated with organ‑related toxicities as determined by clinical chemistry/urinalysis and histopathological examination. The clinical significance of these findings and functional consequences are unknown.

In the 39‑week repeat dose toxicity study in monkeys, pegvaliase-pqpz 3 mg/kg subcutaneously twice weekly (2 times the human steady state AUC at the maximum recommended daily dose) produced systemic arteritis involving small arteries and arterioles in a wide range of organs and tissues (kidney, urinary bladder, pancreas, gallbladder, esophagus, stomach, duodenum, jejunum, ileum, cecum, colon, rectum, lung, heart, sciatic nerve, lacrimal gland, mandibular lymph node, epididymis, seminal vesicle, ovary, uterus, cervix, and vagina) and in subcutaneous injection sites. Arteritis was likely due to the immune-mediated response (e.g., immune complex deposition in blood vessels) associated with chronic administration of a foreign protein to the animals. The incidence and severity of systemic arteritis was dose-dependent. The vascular inflammation observed in this study was not associated with organ related toxicities as determined by clinical pathology parameters (hematology, clinical chemistry, and urinalysis) and histopathological examination.

Studies of longer duration in rats and monkeys treated with pegvaliase‑pqpz have not been conducted.

14 CLINICAL STUDIES

Study 301: Induction/Titration/Maintenance Treatment

Study 165‑301 (referred to as Study 301, NCT01819727) was an open-label randomized, multi-center study of adults with PKU to assess safety and tolerability of self-administered Palynziq in an induction/titration/maintenance regimen with a target maintenance dose of 20 mg subcutaneously once daily or 40 mg subcutaneously once daily. At Palynziq treatment initiation, 253 patients demonstrated inadequate blood phenylalanine control (blood phenylalanine concentration greater than 600 micromol/L) on existing management, and 8 patients had blood phenylalanine concentrations less than or equal to 600 micromol/L. Existing management options included prior or current restriction of dietary phenylalanine and protein intake, and/or prior treatment with sapropterin dihydrochloride. Patients previously treated with sapropterin dihydrochloride were required to discontinue use at least 14 days prior to the first dose.

The 261 enrolled patients were aged 16 to 55 years (mean: 29 years) and had a baseline mean (range) blood phenylalanine of 1,233 (285, 2330) micromol/L. One hundred forty nine out of 261 (57%) patients were taking medical food at baseline and 41 out of 261 patients (16%) were on a protein-restricted diet at baseline (defined as receiving greater than 75% of total protein intake from medical food). Patients were randomized (1:1) to one of two target maintenance dosage arms: 20 mg once daily or 40 mg once daily. Patients were titrated to reach their randomized target dosage of 20 mg once daily or 40 mg once daily. The duration of titration varied among patients and was based on patient tolerability. Of the 261 enrolled patients, 195 (75%) patients reached their randomized maintenance dosage (103 in the 20 mg once daily arm, 92 in the 40 mg once daily arm). Among the patients who reached their randomized maintenance dosage, patients in the 20 mg once daily randomized arm reached their maintenance dosage at a median time of 10 weeks (range: 9 to 29 weeks) and patients in the 40 mg once daily arm reached their maintenance dosage at a median time of 11 weeks (range: 10 to 33 weeks).

Of the 261 patients who enrolled in Study 301, 54 (21%) patients discontinued treatment during Study 301, 4 patients completed Study 301 and did not continue to Study 165‑302 (referred to as Study 302, NCT01889862), 152 patients continued to the eligibility period of Study 302, and 51 patients continued directly from Study 301 into the long‑term treatment period of Study 302.

Study 302: Efficacy Assessment

A total of 164 adult patients with PKU who were previously-treated with Palynziq (152 patients from Study 301 and 12 patients from other Palynziq trials) enrolled in Study 302 and continued treatment with Palynziq in Study 302 for up to 13 weeks to assess eligibility for randomized withdrawal period.

Randomized Withdrawal Period

Following this period of up to 13 weeks of additional Palynziq treatment in Study 302, eligibility for entry into the efficacy assessment period (randomized withdrawal period) was determined by whether a patient achieved at least a 20% reduction in blood phenylalanine concentration from pre-treatment baseline (when in previous studies). Eighty‑six out of 164 patients (52%) met this response target and continued into the randomized withdrawal period. In the double-blind, placebo-controlled, randomized withdrawal period, patients were randomized in a 2:1 ratio to either continue their maintenance Palynziq dosage or to receive matching placebo for a total of 8 weeks. The treatment difference in least squares (LS) mean change in blood phenylalanine concentration from the Study 302 randomized withdrawal baseline to randomized withdrawal Week 8 for each randomized study arm is shown in Table 5. Mean blood phenylalanine concentrations at pre-treatment baseline (Study 301 or other Palynziq trials) are also shown in Table 5. At Study 302 randomized withdrawal Week 8, Palynziq‑treated patients (20 mg once daily or 40 mg once daily) maintained their blood phenylalanine concentrations as compared to their randomized withdrawal baseline, whereas patients randomized to matching placebo (20 mg once daily or 40 mg once daily) returned to their pretreatment baseline blood phenylalanine concentrations (Figure 1).

Table 5: Primary Endpoint: LS Mean Change in Blood Phenylalanine Concentration from Randomized Withdrawal Baseline to Week 8 in Adult Patients with PKU – Efficacy Assessment in Study 302
Randomized Study Arm | Blood Phenylalanine Concentration (micromol/L) Mean (SD) |  |  | LS Mean Change from Study 302 Randomized Withdrawal Baseline to Week 8 (95% CI) | Treatment Difference in LS Mean Change (95% CI) P‑value [Based on the mixed model repeated measures (MMRM) method, with treatment arm, visit, and treatment arm-by-visit interaction as factors adjusting for baseline blood phenylalanine concentration.]
Randomized Study Arm | Pre‑treatment Baseline | Study 302 Randomized Withdrawal Baseline | Study 302 Randomized Withdrawal Week 8 | LS Mean Change from Study 302 Randomized Withdrawal Baseline to Week 8 (95% CI) | Treatment Difference in LS Mean Change (95% CI) P‑value [Based on the mixed model repeated measures (MMRM) method, with treatment arm, visit, and treatment arm-by-visit interaction as factors adjusting for baseline blood phenylalanine concentration.]
Palynziq 20 mg once daily | 1450.2 (310.5); n = 29 | 596.8 (582.8); n = 29 | 553.0 (582.4); n = 26 [Patients who did not complete phenylalanine assessment within the window for Week 8 (Day 43 to 56) were excluded.] | -23.3; (-156.2, 109.7) | -973.0; (‑1204.2, ‑741.9); p < 0.0001
Placebo 20 mg once daily | 1459.1 (354.7); n = 14 | 563.9 (504.6); n = 14 | 1509.0 (372.6); n = 13 | 949.8; (760.4, 1139.1) | -973.0; (‑1204.2, ‑741.9); p < 0.0001
Palynziq 40 mg once daily | 1185.8 (344.0); n = 29 | 410.9 (440.0); n = 29 | 566.3 (567.5); n = 23 | 76.3; (-60.2, 212.8) | -588.5; (-830.1, -346.9); p < 0.0001
Placebo 40 mg once daily | 1108.9 (266.8); n = 14 | 508.2 (363.7); n = 14 | 1164.4 (343.3); n = 10 | 664.8; (465.5, 864.1) | -588.5; (-830.1, -346.9); p < 0.0001

Figure 1: Observed Mean (SE) Blood Phenylalanine Concentrations Over Time in Adult Patients with PKU in Study 302

Study 301 and 302 Continuous Treatment

Of 118 patients from Study 301 with a pre‑treatment baseline blood phenylalanine concentration greater than 600 micromol/L who were randomized to and received at least one dose of 20 mg once daily Palynziq, 107 patients, 97 patients, 93 patients, 86 patients, and 77 patients were treated for at least 6 months, 12 months, 18 months, 24 months, and 36 months, respectively. During the continuous treatment period, patients were allowed to dose up to 60 mg once daily based on investigator discretion to achieve blood phenylalanine lowering (for example, to achieve blood phenylalanine concentrations between 120 and 360 micromol/L).

Of the 118 patients, a majority (91 patients, 77%) reached their first response, defined as a blood phenylalanine concentration less than or equal to 600 micromol/L, at a time point prior to 36 months. Of the 91 patients, 9 patients (10%) achieved their first response at a dose less than 20 mg once daily, 44 patients (48%) achieved their first response at a dose of 20 mg once daily, 26 patients (29%) achieved their first response at a dose of 40 mg once daily, and 12 patients (13%) achieved their first response at a dose of 60 mg once daily. Of the 44 patients that achieved their first response at a dose of 20 mg once daily, 36 (82%) achieved it by 24 weeks of treatment. Of the 26 patients that achieved their first response at a dose of 40 mg once daily, 18 (69%) achieved it by 16 weeks of treatment. Of the 12 patients that achieved their first response at a dose of 60 mg once daily, 8 (67%) achieved it by 16 weeks of treatment.

Of the 107 patients treated for at least 6 months, 28 (26%), 18 (17%), and 11 (10%) had a blood phenylalanine concentration less than or equal to 600, 360, and 120 micromol/L, respectively, at 6 months of treatment. Of the 97 patients treated for at least 12 months, 47 (48%), 41 (42%), and 31 (32%) had a blood phenylalanine concentration less than or equal to 600, 360, and 120 micromol/L, respectively, at 12 months of treatment. Of the 93 patients treated for at least 18 months, 64 (69%), 46 (49%), and 36 (39%) had a blood phenylalanine concentration less than or equal to 600, 360, and 120 micromol/L, respectively, at 18 months of treatment. Of the 86 patients treated for at least 24 months, 65 (76%), 57 (66%), and 43 (50%) had a blood phenylalanine concentration less than or equal to 600, 360, and 120 micromol/L, respectively, at 24 months of treatment. Of the 77 patients treated for at least 36 months, 58 (75%), 51 (66%), and 37 (48%) had a blood phenylalanine concentration less than or equal to 600, 360, and 120 micromol/L, respectively, at 36 months of treatment.

16 HOW SUPPLIED/STORAGE AND HANDLING

How Supplied

Palynziq (pegvaliase-pqpz) injection is supplied as a preservative-free, sterile, clear to slightly opalescent, colorless to pale yellow solution. All dosage strengths of Palynziq are provided in a 1 mL glass syringe with a 26 gauge, 0.5 inch needle.

Each carton contains 1 or 10 trays with single-dose prefilled syringe(s), Prescribing Information, Medication Guide, and Instructions for Use. The following packaging configurations are available.

Table 6: Palynziq Packaging Configurations
Pegvaliase‑pqpz 2.5 mg/0.5 mL | 1 syringe/carton | NDC 68135‑058‑90
Pegvaliase‑pqpz 10 mg/0.5 mL | 1 syringe/carton | NDC 68135‑756‑20
Pegvaliase‑pqpz 20 mg/mL | 1 syringe/carton; 10 syringes/carton | NDC 68135‑673‑40; NDC 68135‑673‑45

Storage and Handling

- Store in refrigerator at 36°F to 46°F (2°C to 8°C) in its original carton to protect from light.
- Do not freeze or shake.
- For patients: If needed, store Palynziq in the original carton at room temperature between 68°F to 77°F (20°C to 25°C) for up to 30 days. Record the date removed from refrigeration on the carton. Once stored at room temperature, do not return the product to the refrigerator.
- The shelf-life expires after storage at room temperature for 30 days, or after the expiration date on the product carton, whichever is earlier.

17 PATIENT COUNSELING INFORMATION

Advise the patient to read the FDA-approved patient labeling (Medication Guide and Instructions for Use).

Anaphylaxis and Other Hypersensitivity Reactions

- Advise patients that Palynziq may cause hypersensitivity reactions, including anaphylaxis that can occur at any time. Instruct patients to recognize the signs and symptoms of anaphylaxis [see Warnings and Precautions (5.1, 5.3)].
- Instruct patients to carry auto-injectable epinephrine with them at all times during Palynziq treatment. Instruct the patient and observer (if applicable) on the appropriate use of auto‑injectable epinephrine for anaphylaxis [see Warnings and Precautions (5.1)].
- Instruct patients who experience anaphylaxis to seek immediate medical care, discontinue therapy, and resume treatment only at the instruction of a healthcare provider [see Warnings and Precautions (5.1)].

Palynziq REMS Program

Palynziq is available only through a restricted program called the Palynziq REMS [see Warnings and Precautions (5.2)]. Inform the patient of the following notable requirements:

- Patients must be enrolled in the Palynziq REMS.
- Patients must be educated about the risk of anaphylaxis by a certified prescriber to ensure they understand the risks and benefits of treatment with Palynziq.
- Patients must fill a prescription for auto-injectable epinephrine and carry it with them at all times.
- Patients will be given a Palynziq Patient Wallet Card that they should carry with them at all times. This card describes symptoms which, if experienced, should prompt the patient and observer (if applicable) to immediately seek medical care. Advise the patient to show the Palynziq Wallet Card to other treating healthcare providers.

Palynziq is available only from certified pharmacies participating in the program. Therefore, provide patients with the telephone number and website for information on how to obtain the product.

Administration

- Advise patients to monitor their dietary protein and phenylalanine intake throughout treatment with Palynziq, and adjust intake as directed by their healthcare provider based on blood phenylalanine concentrations [see Dosage and Administration (2.2)].
- Provide appropriate instruction for methods of self-injection, including careful review of the Palynziq Medication Guide and Instructions for Use. Instruct patients in the use of aseptic technique when administering Palynziq [see Dosage and Administration (2.4)].
- Inform patients that a healthcare provider will show them or their caregiver how to prepare to inject Palynziq before self-administering.
- Advise patients not to inject into moles, scars, birthmarks, bruises, rashes, or areas where the skin is hard, tender, red, damaged, burned, inflamed, or tattooed.
- Advise patients to rotate areas of injection with each dose.
- Advise patients that injection site infections may occur and to check the injection site for redness, swelling, or tenderness prior to injection. Instruct patients to contact their healthcare provider if signs or symptoms of an infection develop, persist, or worsen [see Warnings and Precautions (5.4)].
- Advise patients to not administer Palynziq into the affected area until the infection has resolved.
- Advise patients to follow sharps disposal recommendations [see Instructions for Use] patients on safe disposal procedures.
- Advise patients that the shelf‑life expires after storage at room temperature for 30 days or after the expiration date on the product carton, whichever is earlier.

Pregnancy

- Advise pregnant women and females of reproductive potential of the potential risk to a fetus. Advise females to inform their healthcare provider of a known or suspected pregnancy [see Use in Specific Populations (8.1)].
- Advise women who are exposed to Palynziq during pregnancy or who become pregnant within one month following the last dose of Palynziq that there is a pregnancy surveillance program that monitors pregnancy outcomes. Encourage these patients to report their pregnancy to BioMarin (1‑866‑906‑6100) [see Use in Specific Populations (8.1)].

Manufactured by:

BioMarin Pharmaceutical Inc.

Novato, CA 94949

US License No. 1649

MEDICATION GUIDE

Palynziq® (Pal-lin-zeek)

(pegvaliase-pqpz)

Injection, for subcutaneous use

What is the most important information I should know about Palynziq?

Palynziq can cause a severe allergic reaction (anaphylaxis) that may be life-threatening and can happen any time during treatment with Palynziq. Severe allergic reactions are a serious but common side effect of Palynziq.

- You will receive your first injection of Palynziq in a healthcare setting where you will be closely watched for at least 1 hour after your injection for a severe allergic reaction.
- If you have a severe allergic reaction during treatment with Palynziq, you will need to receive an auto-injection of epinephrine immediately and get emergency medical help right away.
- Your healthcare provider will decide if you (or your caregiver) are able to give the Palynziq injections, recognize the signs and symptoms of a severe allergic reaction, give an injection of epinephrine and call for emergency medical help, if needed.
- Your healthcare provider may recommend that an adult observer (or your caregiver) be with you when you give your Palynziq injection, and for at least 1 hour after your injection to watch you for signs and symptoms of a severe allergic reaction and, if needed, give you an injection of epinephrine and call for emergency medical help.

Stop injecting Palynziq and get emergency medical care right away if you have any of the following symptoms of a severe allergic reaction during treatment with Palynziq:

- fainting (passing out)
- dizziness or lightheadedness
- sudden confusion
- trouble breathing or wheezing
- chest discomfort or chest tightness
- fast heart rate

- swelling of your face, lips, eyes, or tongue
- throat tightness
- flushed skin
- skin rash, itching, or raised bumps on skin
- nausea, vomiting, or diarrhea
- losing control of urine or stools

- Your healthcare provider will prescribe an auto-injectable epinephrine for you and will teach you (or your caregiver) and your observer, if needed, when and how to use it if you have a severe allergic reaction. Keep the auto-injectable epinephrine with you at all times during treatment with Palynziq. Read the Patient Information that comes with the auto-injectable epinephrine that your healthcare provider prescribes for you for more information.
- If you have a severe allergic reaction, do not continue to take Palynziq until you talk with your healthcare provider. Tell your healthcare provider that you had a severe allergic reaction. Your healthcare provider will tell you if you can continue treatment with Palynziq.
  - Your healthcare provider may prescribe other medicines to take before your Palynziq injection that may help reduce the symptoms of an allergic reaction.
  - If your healthcare provider decides that you can continue treatment with Palynziq after a severe allergic reaction, you will receive your next injection of Palynziq in a healthcare setting where you will be closely watched for at least 1 hour after your injection for a severe allergic reaction.
- Your healthcare provider will give you a Palynziq Patient Wallet Card that describes symptoms that you (or your caregiver), or your observer, should know that require you to get emergency medical care right away. Carry this card with you at all times during treatment with Palynziq. It is important to show your Palynziq Patient Wallet Card to any other healthcare provider who treats you.

Palynziq is only available through a restricted program called the Palynziq Risk Evaluation and Mitigation Strategy (REMS) Program. Before you can receive Palynziq, you must:

- enroll in this program.
- receive education about the risk of a severe allergic reaction (anaphylaxis) by a healthcare provider certified in the Palynziq REMS to be sure that you understand the risks and benefits of treatment with Palynziq.
- fill the prescription your healthcare provider gives you for the auto-injectable epinephrine and carry it with you at all times during treatment with Palynziq.
- carry the Palynziq Patient Wallet Card with you at all times.

Talk to your healthcare provider for more information about the Palynziq REMS and how to enroll.

What is Palynziq?

Palynziq is a prescription medicine used to lower blood levels of phenylalanine in adults with PKU (phenylketonuria) who have uncontrolled blood phenylalanine levels above 600 micromol/L (10 mg/dL) on their current treatment.

It is not known if Palynziq is safe and effective in children.

Before injecting Palynziq, tell your healthcare provider about all of your medical conditions, including if you:

- cannot or are not willing to use auto-injectable epinephrine to treat a severe allergic reaction.
- are pregnant or plan to become pregnant. Palynziq may harm your unborn baby. Tell your healthcare provider right away if you become pregnant or think you might be pregnant while taking Palynziq.
  - If your phenylalanine levels are too high or too low during pregnancy, this may also affect your unborn baby. You and your healthcare provider can decide the best way for you to manage your blood phenylalanine levels and discuss the risks and benefits of taking Palynziq during pregnancy to you and your unborn baby. It is very important to keep your phenylalanine levels at the levels your healthcare provider recommends during pregnancy.
  - Pregnancy Surveillance Program. There is a pregnancy surveillance program for females who take Palynziq during pregnancy, or who become pregnant while receiving Palynziq or within 1 month after their last dose of Palynziq. The purpose of this program is to collect information about the health of you and your baby while taking Palynziq. Talk to your healthcare provider about how you can take part in this program or call BioMarin at 1-866-906-6100.
- are breastfeeding or plan to breastfeed. It is not known if Palynziq passes into your breast milk. Talk to your healthcare provider about the best way to feed your baby if you take Palynziq.

Tell your healthcare provider about all the medicines you take, including prescription and over-the-counter medicines, vitamins, or herbal supplements.

How should I take Palynziq?

- Your healthcare provider will give you the Palynziq injection until they decide that you (or your caregiver) can give it. See “What is the most important information I should know about Palynziq?”
- Your healthcare provider may prescribe medicine for you to take before your Palynziq injection to help reduce the symptoms of an allergic reaction.
- If your healthcare provider decides that you (or your caregiver) can give your Palynziq injections, you (or your caregiver) will be shown how to prepare and give your Palynziq injections. See the “Instructions for Use” for detailed instructions on how to prepare and give an injection of Palynziq.
- Use Palynziq exactly as your healthcare provider tells you to. Your healthcare provider will tell you how much Palynziq to inject and when to inject it.
- Palynziq comes in prefilled syringes with 3 different strengths (2.5 mg, 10 mg, or 20 mg). You may need more than 1 Palynziq prefilled syringe for your prescribed dose.
- Monitor the amount of protein and phenylalanine that you eat or drink. Your healthcare provider may change the amount of protein and phenylalanine you should have in your diet during treatment with Palynziq, depending on the levels of phenylalanine in your blood. Follow your healthcare provider’s instructions about the amount of protein and phenylalanine you should have in your diet.
- If you miss a dose, take your next dose at the regular time. Do not take two doses of Palynziq to make up for a missed dose.

What are the possible side effects of Palynziq?

Palynziq may cause serious side effects, including:

- See “What is the most important information I should know about Palynziq?”
- Other allergic reactions to Palynziq can happen during treatment with Palynziq. Contact your healthcare provider right away if you have any of the following symptoms of an allergic reaction including: rash, itching, or swelling of the face, lips, eyes, or tongue. Your healthcare provider may change your dose of Palynziq, stop your treatment with Palynziq for a period of time, or prescribe medicine for you to take before your Palynziq injection to help reduce the symptoms of an allergic reaction.
- Injection site infections. Serious infections at the injection site have happened in people during treatment with Palynziq. Some of these injection site infections required hospitalization, surgery, treatment with antibiotics given through the vein, or stopping treatment with Palynziq. Change (rotate) your injection site and check your injection site for redness, swelling, or tenderness before each injection. Tell your healthcare provider right away if you develop signs or symptoms of an infection at your injection site that are new, do not go away, or get worse, including:

◦ pain, redness, swelling, or tenderness
◦ the area feels hard
◦ fluid or pus

◦ blisters
◦ a dark scab
◦ an open wound

Do not inject Palynziq into the affected area until the infection has cleared.

The most common side effects of Palynziq include:

- injection site reactions, such as redness, itching, pain, bruising, rash, swelling, tenderness
- joint pain
- headache
- skin reactions that spread on your skin and last at least 14 days, such as itching, rash, redness
- nausea
- stomach pain
- vomiting

- cough
- mouth and throat pain
- itching
- diarrhea
- stuffy nose
- feel very tired
- dizziness
- anxiety
- low levels of phenylalanine in your blood

These are not all the possible side effects of Palynziq. Call your doctor for medical advice about side effects. You may report side effects to FDA at 1-800-FDA-1088.

How should I store Palynziq?

- Store Palynziq in the refrigerator at 36°F to 46°F (2°C to 8°C).
- If needed, you may store Palynziq at room temperature between 68°F to 77°F (20°C to 25°C) for up to 30 days.
  - Write the date that you remove Palynziq from the refrigerator on the carton.
  - If stored at room temperature, do not put Palynziq back in the refrigerator.
- Keep Palynziq in the original carton to protect from light.
- Do not freeze or shake Palynziq.
- Throw away Palynziq if it has been kept at room temperature for 30 days and has not been used, or after the expiration date on the carton, whichever comes first.

Keep Palynziq and all medicines out of the reach of children.

General Information about the safe and effective use of Palynziq.

Medicines are sometimes prescribed for purposes other than those listed in a Medication Guide. Do not use Palynziq for a condition for which it was not prescribed. Do not give Palynziq to other people, even if they have the same symptoms that you have. It may harm them. You can ask your pharmacist or healthcare provider for information about Palynziq that is written for health professionals.

What are the ingredients in Palynziq?

Active ingredients: pegvaliase-pqpz

Inactive ingredients: sodium chloride, trans-cinnamic acid, tromethamine, and tromethamine hydrochloride

Manufactured by: BioMarin Pharmaceutical Inc. Novato, CA 94949 US License No. 1649

For more information, go to http://www.Palynziq.com/ or call 1-866-906-6100.

This Medication Guide has been approved by the U.S. Food and Drug Administration.

Revised: 10/2025

INSTRUCTION FOR USE

Instructions for Use

Palynziq (Pal-lin-zeek)

(pegvaliase-pqpz)

Injection for Subcutaneous Use

Single-Dose Prefilled Syringe

Read this Instructions for Use before you start using the Palynziq prefilled syringe and each time you get a new prescription. There may be new information. This information does not take the place of talking to your healthcare provider about your medical condition or your treatment.

Follow these instructions carefully while you are using Palynziq. If your healthcare provider decides that you (or your caregiver) can give the injections of Palynziq at home, your healthcare provider will show you (or your caregiver) how to inject Palynziq the right way. Your healthcare provider should watch you (or your caregiver) give the first Palynziq injection and monitor you for signs and symptoms of a severe allergic reaction (anaphylaxis). Do not inject Palynziq until your healthcare provider shows you (or your caregiver) how to inject Palynziq the right way and has watched you (or your caregiver) give your injection.

Talk to your healthcare provider if you (or your caregiver) have any questions about how to inject Palynziq the right way.

Do not share your prefilled syringes with anyone else. You may give an infection to them or get an infection from them.

Store your Palynziq prefilled syringe(s) in its original carton in the refrigerator. See “Storage of Palynziq” at the end of this Instructions for Use.

Supplies you will need for each injection of Palynziq (See Figure A):

- Palynziq prefilled syringe(s) in sealed tray(s). Each tray contains 1 prefilled syringe. You may need more than 1 prefilled syringe for your prescribed dose.
- 1 gauze pad or cotton ball
- 1 alcohol pad
- 1 bandage
- 1 puncture resistant or sharps disposal container. See “Dispose of the used prefilled syringes” at the end of this Instructions for Use.

Figure A

Important things to know about using your Palynziq prefilled syringe:

- Inject only 1 time with each Palynziq prefilled syringe. Do not use a Palynziq syringe more than 1 time.
- Do not pull back on the plunger at any time.
- Do not remove the needle cap until you are ready to inject.

Figure B below shows what the prefilled syringe looks like before use.

Figure B

Select the correct Palynziq prefilled syringe(s) for your dose. You may need more than 1 prefilled syringe for your prescribed dose. Your healthcare provider will tell you which syringe(s) to use. Ask your healthcare provider if you have any questions.

When you receive your Palynziq prefilled syringe(s), check that the name “Palynziq" appears on the carton(s).

- Palynziq prefilled syringes come in 3 different strengths (See Figure C).
- Before you inject Palynziq, check each carton and syringe to make sure you have the right prefilled syringe for your prescribed dose.

Figure C

Set up your injection

Step 1: Gather your supplies for the injection(s) (See Figure A) and place them on a clean flat surface.

Take out the number of cartons needed for your prescribed dose from the refrigerator.

Check the expiration date (EXP) on the carton(s) (See Figure D).

- If the expiration date has passed, do not use the prefilled syringe(s) in that carton. Call BioMarin at 1‑866‑906‑6100 or your healthcare provider for help with Palynziq.

Figure D

Step 2: Open the carton(s) and take out the sealed tray(s) that you need for your prescribed dose (See Figure E). You may need more than 1 prefilled syringe for your prescribed dose.

Place the sealed tray(s) on a clean, flat surface out of reach of children and pets.

Put the carton with any remaining trays back in the refrigerator.

Figure E

Step 3: Let the sealed tray(s) sit at room temperature for at least 30 minutes. Injecting Palynziq when cold can make the injection feel uncomfortable.

- Do not warm up the prefilled syringe in any other way other than letting it sit at room temperature. Do not warm in a microwave and do not place in hot water.

Let the sealed tray(s) sit at room temperature for at least 30 minutes before opening.

Step 4: Peel off the cover from the tray (See Figure F).

Figure F

Step 5: Hold the middle of the prefilled syringe body and remove the prefilled syringe from the tray (See Figure G).

- Throw away the prefilled syringe if it looks damaged or used, and use a new prefilled syringe for your injection. See “Dispose of the used prefilled syringes” at the end of this Instructions for Use. Call BioMarin at 1‑866‑906‑6100 or your healthcare provider for help with Palynziq.
- Do not remove the needle cap from the prefilled syringe until Step 12.
- Do not shake or roll the syringe in your hands.

Figure G

Step 6: Check the prefilled syringe label to make sure you have the correct strength for your prescribed dose.

Check the prefilled syringe label to make sure you have the correct strength.

Step 7: Look at the liquid through the viewing window (See Figure H).

- It is normal to see air bubbles. Do not flick or try to push the bubbles out.

The liquid should look clear and colorless to pale yellow. Throw away the prefilled syringe if the liquid is cloudy, discolored, or has particles in it and use a new prefilled syringe for your injection. See “Dispose of the used prefilled syringes” at the end of this Instructions for Use. Call BioMarin at 1‑866‑906‑6100 or your healthcare provider for help with Palynziq.

Figure H

Choose and prepare injection site

Step 8: Choose your injection site.

The recommended injection sites are:

- Front middle of the thighs.
- The abdomen except for the 2 inch (5 centimeter) area directly around the belly button (navel).

Figure I

If a caregiver is giving the injection, the top of the buttocks and the back of the upper arms may also be used (See Figure I).

- Do not inject into moles, scars, birthmarks, bruises, rashes, or areas where the skin is hard, tender, red, damaged, burned, inflamed, or tattooed.
- If you need more than 1 injection for your dose, the injection sites should be at least 2 inches away from each other. The second injection site can be on the same part of the body or a different part of the body (See Figures I and J).
- For each injection, change (rotate) your injection sites. Choose an injection site that is at least 2 inches away from the injection site that you used for the last injection. It can be on the same part of the body or a different part of the body (See Figures I and J).

Figure J

Inject at least 2 inches apart

Step 9: Wash your hands well with soap and water before injecting Palynziq (See Figure K).

Figure K

Step 10: Clean the chosen site with an alcohol pad. Let the skin air dry for at least 10 seconds before injecting Palynziq (See Figure L).

- Do not touch the cleaned injection site.
- Do not remove the needle cap until you are ready to inject Palynziq.

Figure L

Inject Palynziq

Step 11: Hold the body of the prefilled syringe with 1 hand with the needle facing away from you (See Figure M).

- Do not use the prefilled syringe if it is dropped. Throw away the prefilled syringe if it is dropped and use a new prefilled syringe for your injection. See “Dispose of the used prefilled syringes” at the end of this Instructions for Use. Call BioMarin at 1‑866‑906‑6100 or your healthcare provider for help with Palynziq.

Figure M

Step 12: Pull the needle cap straight off the needle (See Figure N).

- Do not twist the needle cap during removal.
- Do not hold the prefilled syringe by the plunger or plunger head while taking the needle cap off.
- Before injecting Palynziq, check to make sure that the needle is not damaged or bent. Throw away the prefilled syringe if the needle is damaged or bent and use a new prefilled syringe for your injection. See “Dispose of the used prefilled syringes” at the end of this Instructions for Use. Call BioMarin at 1‑866‑906‑6100 or your healthcare provider for help with Palynziq.

You may see a drop of liquid on the tip of the needle. This is normal. Do not wipe it away. Throw the needle cap away in a puncture resistant or sharps disposal container.

Figure N

Step 13: Hold the body of the prefilled syringe in 1 hand between your thumb and index finger. Use your other hand to pinch up the skin around the injection site. Hold the skin firmly (See Figure O).

- Do not touch the plunger head while inserting the needle into the skin.

Figure O

Step 14: Use a quick motion to fully insert the needle into the pinched skin at a 45 to 90 degree angle (See Figure P).

Release the pinch of skin. Use that hand to hold the bottom of the prefilled syringe steady. Place the thumb of your other hand on the plunger head and place your index and middle fingers under the finger grips (See Figure P).

Figure P

Step 15: Use your thumb to push in the plunger slowly and steadily as far as it will go to inject all the medicine (See Figure Q). More pressure on the plunger may be needed to inject all the medicine for the 10 mg and 20 mg strength prefilled syringes.

Figure Q

Step 16: Slowly move your thumb up to release the plunger. The needle will automatically be covered by the prefilled syringe body (See Figure R).

Figure R

Treat injection site

Step 17: Treat injection site (if needed).

If you see drops of blood at the injection site, press a cotton ball or gauze over the injection site and hold for about 10 seconds. You may cover the injection site with a small adhesive bandage if needed.

If more than 1 prefilled syringe is needed for your prescribed dose:

Step 18: If your healthcare provider tells you to use more than 1 prefilled syringe for your prescribed dose, repeat Steps 4 to 17 listed above for each prefilled syringe that you use.

- Note: Do not give the injection in the same spot. The injection sites should be at least 2 inches away from each other. See Step 8 for information on choosing an injection site.

If you need to use more than 1 prefilled syringe for your prescribed dose, repeat Steps 4 to 17 right away for each prefilled syringe you use.

Dispose of the used prefilled syringes

Step 19: Put your used prefilled syringes in a puncture resistant container, such as an FDA‑cleared sharps disposal container immediately after use (See Figure S).

Do not throw away (dispose of) prefilled syringes in your household trash.

If you do not have an FDA-cleared sharps disposal container, you may use a household container that is:

- made of a heavy-duty plastic,
- can be closed with a tight-fitting, puncture-resistant lid, without sharps being able to come out,
- upright and stable during use,
- leak-resistant, and
- properly labeled to warn of hazardous waste inside the container.

When your sharps disposal container is almost full, you will need to follow your community guidelines for the right way to dispose of your sharps disposal container. There may be state or local laws about how you should throw away used needles and syringes. For more information about safe sharps disposal and for specific information about sharps disposal in the state that you live in, go to the FDA’s website at: http://www.fda.gov/safesharpsdisposal

Do not dispose of your used sharps disposal container in your household trash unless your community guidelines permit this. Do not recycle your used sharps disposal container.

Note: Keep sharps disposal container out of the reach of children and pets.

Figure S

Storage of Palynziq

Figure T

- Store Palynziq in the refrigerator at 36°F to 46°F (2°C to 8°C) (See Figure T).
- If needed, you may store Palynziq at room temperature between 68°F to 77°F (20°C to 25°C) for up to 30 days.
- Write the date that you remove Palynziq from the refrigerator on the carton.
- If stored at room temperature, do not put Palynziq back in the refrigerator.
- Keep Palynziq in the original carton to protect from light.
- Do not freeze or shake Palynziq.
- Throw away Palynziq if it has been kept at room temperature for 30 days and has not been used, or after the expiration date on the carton, whichever comes first.

Keep Palynziq and all medicines out of the reach of children.

This Instructions for Use has been approved by the U.S. Food and Drug Administration.

Manufactured by:

BioMarin Pharmaceutical Inc.

Novato, CA 94949

U.S. License No. 1649

Revised: 10/2020

PALYNZIQ - 2.5 MG/0.5 ML

NDC 68135-058-90 Rx only

PalynziqTM

(pegvaliase-pqpz)

Injection

2.5 mg/0.5 mL

For Subcutaneous Use Only

Contains one x 2.5 mg/0.5 mL single-dose prefilled syringe.

Discard after use.

ATTENTION: Dispense the enclosed Medication Guide to each patient.

PALYNZIQ - 10 MG/0.5ML

NDC 68135-756-20 Rx only

PalynziqTM

(pegvaliase-pqpz)

Injection

10 mg/0.5 mL

For Subcutaneous Use Only

Contains one x 10 mg/0.5 mL single-dose prefilled syringe.

Discard after use.

ATTENTION: Dispense the enclosed Medication Guide to each patient.

PALYNZIQ (SINGLE PACK) - 20 MG/ML

NDC 68135-673-40 Rx only

PalynziqTM

(pegvaliase-pqpz)

Injection

20 mg/mL

For Subcutaneous Use Only

Contains one x 20 mg/mL single-dose prefilled syringe.

Discard after use.

ATTENTION: Dispense the enclosed Medication Guide to each patient.

PALYNZIQ (MULTI-PACK) - 20 MG/ML

NDC 68135-673-45 Rx only

PalynziqTM

(pegvaliase-pqpz)

Injection

20 mg/mL

For Subcutaneous Use Only

Contains ten 20 mg/mL single-dose prefilled syringes.

Discard after use.

ATTENTION: Dispense the enclosed Medication Guide to each patient.